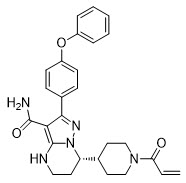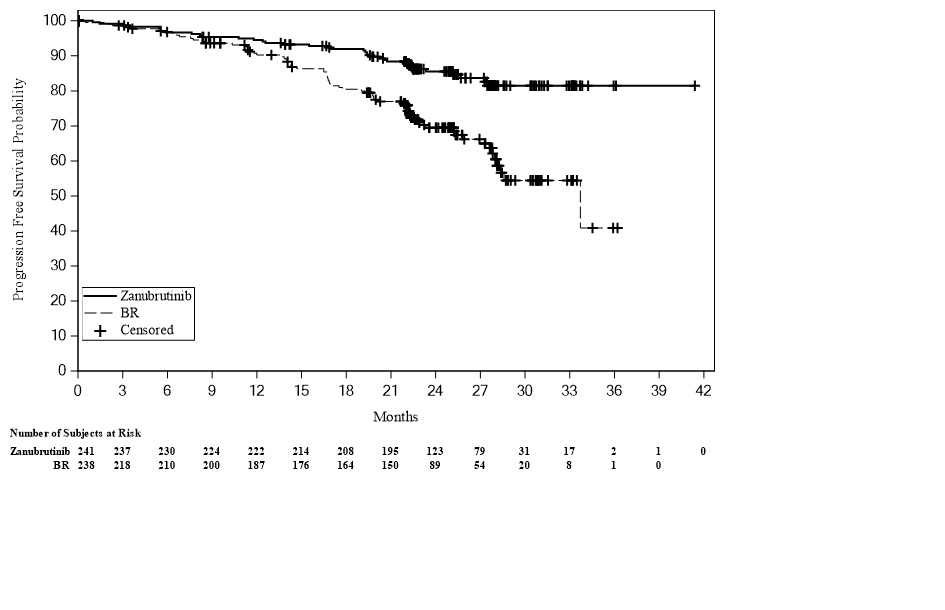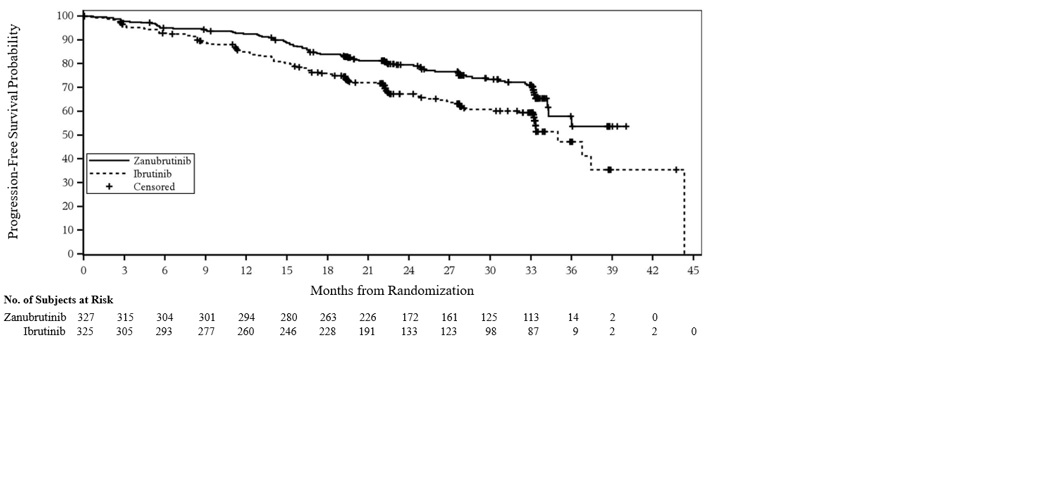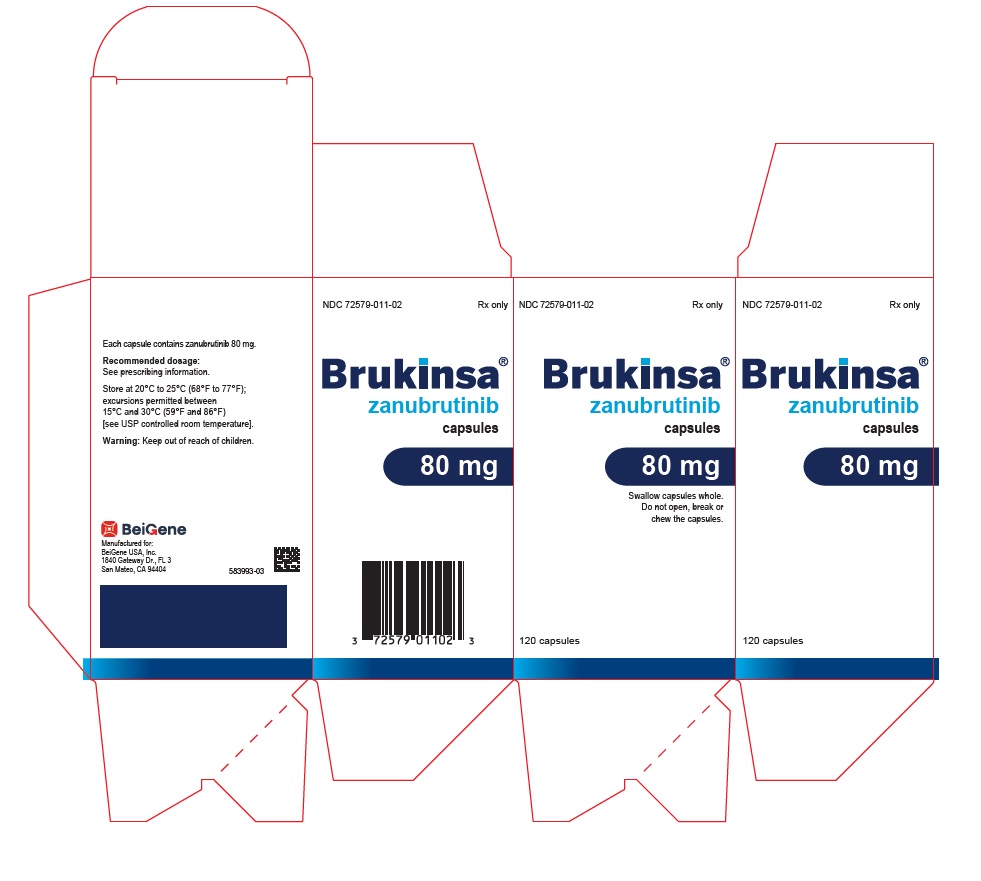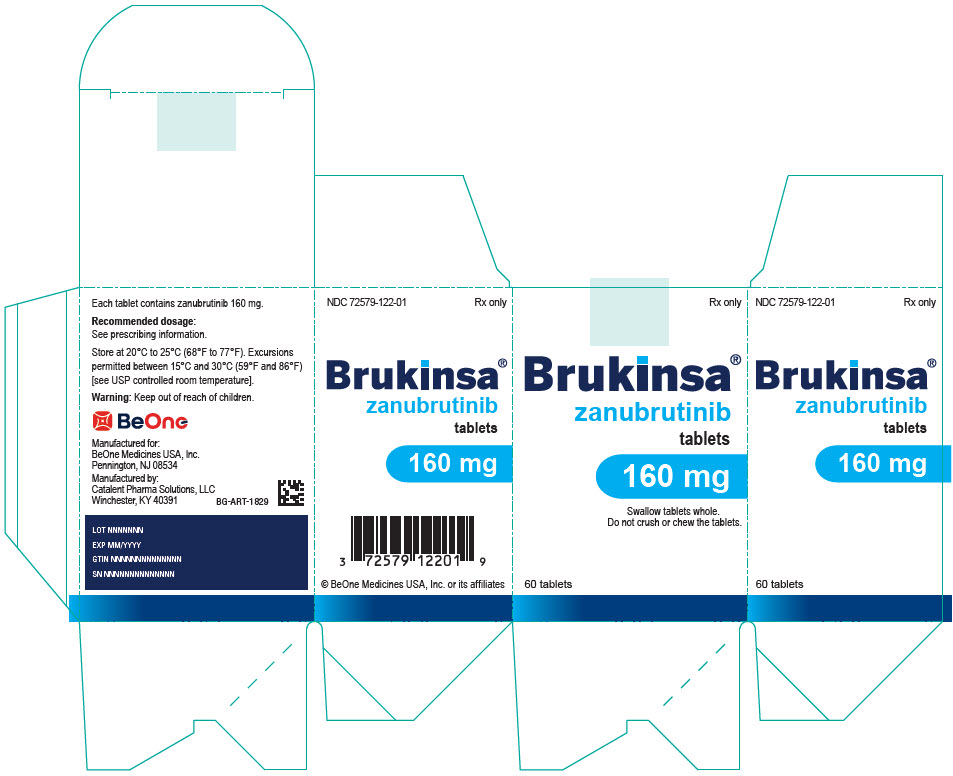 DRUG LABEL: BRUKINSA
NDC: 72579-011 | Form: CAPSULE
Manufacturer: BeOne Medicines USA, Inc.
Category: prescription | Type: HUMAN PRESCRIPTION DRUG LABEL
Date: 20260202

ACTIVE INGREDIENTS: ZANUBRUTINIB 80 mg/1 1
INACTIVE INGREDIENTS: SILICON DIOXIDE; CROSCARMELLOSE SODIUM; MAGNESIUM STEARATE; MICROCRYSTALLINE CELLULOSE; SODIUM LAURYL SULFATE; GELATIN, UNSPECIFIED; TITANIUM DIOXIDE; FERROSOFERRIC OXIDE

HIGHLIGHTS OF PRESCRIBING INFORMATION

These highlights do not include all the information needed to use BRUKINSA safely and effectively. See full prescribing information for BRUKINSA.
BRUKINSA® (zanubrutinib) capsules, for oral use
BRUKINSA® (zanubrutinib) tablets, for oral use
Initial U.S. Approval: 2019

RECENT MAJOR CHANGES

Dosage and Administration, Recommended Dosage (2.1) | 6/2025
Dosage and Administration, Dosage Modification for Use in Hepatic Impairment (2.2) | 6/2025

1 INDICATIONS AND USAGE

BRUKINSA is a kinase inhibitor indicated for the treatment of adult patients with:

- Mantle cell lymphoma (MCL) who have received at least one prior therapy. (1.1)
  This indication is approved under accelerated approval based on overall response rate. Continued approval for this indication may be contingent upon verification and description of clinical benefit in a confirmatory trial.
- Waldenström's macroglobulinemia (WM). (1.2)
- Relapsed or refractory marginal zone lymphoma (MZL) who have received at least one anti–CD20-based regimen. (1.3)
  This indication is approved under accelerated approval based on overall response rate. Continued approval for this indication may be contingent upon verification and description of clinical benefit in a confirmatory trial.
- Chronic lymphocytic leukemia (CLL) or small lymphocytic lymphoma (SLL). (1.4)
- Relapsed or refractory follicular lymphoma (FL), in combination with obinutuzumab, after two or more lines of systemic therapy. (1.5)
  This indication is approved under accelerated approval based on response rate and durability of response. Continued approval for this indication may be contingent upon verification and description of clinical benefit in a confirmatory trial.

2 DOSAGE AND ADMINISTRATION

- Recommended dosage: 160 mg orally twice daily or 320 mg orally once daily with or without food; swallow whole with water.
- Tablets can be split in half as prescribed by the healthcare provider. (2.1)
- Reduce BRUKINSA dose in patients with severe hepatic impairment. (2.2, 8.7)
- Advise patients not to open, break, or chew capsules. (2.1)
- Advise patients not to chew or crush tablets. (2.1)
- Manage toxicity using treatment interruption, dose reduction, or discontinuation. (2.4)

3 DOSAGE FORMS AND STRENGTHS

- Capsules: 80 mg. (3)
- Tablets: 160 mg with functional scoring. (3)

4 CONTRAINDICATIONS

None. (4)

5 WARNINGS AND PRECAUTIONS

- Hemorrhage: Monitor for bleeding and manage appropriately. (5.1)
- Infections: Monitor patients for signs and symptoms of infection, including opportunistic infections, and treat as needed. (5.2)
- Cytopenias: Monitor complete blood counts during treatment. (5.3)
- Second Primary Malignancies: Other malignancies have developed including skin cancers and non-skin carcinomas. Monitor and advise patients to use sun protection. (5.4)
- Cardiac Arrhythmias: Monitor for signs and symptoms of arrhythmias and manage appropriately. (5.5)
- Hepatotoxicity, Including Drug-Induced Liver Injury: Monitor hepatic function throughout treatment. (5.6)
- Embryo-Fetal Toxicity: Can cause fetal harm. Advise women of the potential risk to a fetus and to use effective contraception. (5.7)

6 ADVERSE REACTIONS

The most common adverse reactions (≥30%), including laboratory abnormalities, are neutrophil count decreased, platelet count decreased, upper respiratory tract infection, hemorrhage, and musculoskeletal pain. (6.1)

To report SUSPECTED ADVERSE REACTIONS, contact BeOne Medicines at 1-877-828-5596 or FDA at 1-800-FDA-1088 or www.fda.gov/medwatch.

7 DRUG INTERACTIONS

- CYP3A Inhibitors: Modify BRUKINSA dose with moderate or strong CYP3A inhibitors as described. (2.3, 7.1)
- CYP3A Inducers: Avoid coadministration with strong or moderate CYP3A inducers. Dose adjustment may be recommended with moderate CYP3A inducers. (2.3, 7.1)

8 USE IN SPECIFIC POPULATIONS

Lactation: Advise not to breastfeed. (8.2)

FULL PRESCRIBING INFORMATION

1 INDICATIONS AND USAGE

1.1 Mantle Cell Lymphoma

BRUKINSA is indicated for the treatment of adult patients with mantle cell lymphoma (MCL) who have received at least one prior therapy.

This indication is approved under accelerated approval based on overall response rate [see Clinical Studies (14.1)]. Continued approval for this indication may be contingent upon verification and description of clinical benefit in a confirmatory trial.

1.2 Waldenström's Macroglobulinemia

BRUKINSA is indicated for the treatment of adult patients with Waldenström's macroglobulinemia (WM) [see Clinical Studies (14.2)].

1.3 Marginal Zone Lymphoma

BRUKINSA is indicated for the treatment of adult patients with relapsed or refractory marginal zone lymphoma (MZL) who have received at least one anti–CD20-based regimen.

This indication is approved under accelerated approval based on overall response rate [see Clinical Studies (14.3)]. Continued approval for this indication may be contingent upon verification and description of clinical benefit in a confirmatory trial.

1.4 Chronic Lymphocytic Leukemia or Small Lymphocytic Lymphoma

BRUKINSA is indicated for the treatment of adult patients with chronic lymphocytic leukemia (CLL) or small lymphocytic lymphoma (SLL) [see Clinical Studies (14.4)].

1.5 Follicular Lymphoma

BRUKINSA is indicated for the treatment of adult patients with relapsed or refractory follicular lymphoma (FL), in combination with obinutuzumab, after two or more lines of systemic therapy.

This indication is approved under accelerated approval based on response rate and durability of response [see Clinical Studies (14.5)]. Continued approval for this indication may be contingent upon verification and description of clinical benefit in a confirmatory trial.

2 DOSAGE AND ADMINISTRATION

2.1 Recommended Dosage

The recommended dosage of BRUKINSA for monotherapy or in combination with obinutuzumab is 160 mg taken orally twice daily or 320 mg taken orally once daily until disease progression or unacceptable toxicity.

Capsule Administration Instructions

- Administer BRUKINSA capsules with or without food [see Clinical Pharmacology (12.3)]. Advise patients to swallow capsules whole with water and not to open, break, or chew capsules.

Tablet Administration Instructions

- Administer BRUKINSA tablets with or without food [see Clinical Pharmacology (12.3)]. Advise patients to swallow tablets whole with water and not to chew or crush the tablets. The tablets can be split in half as prescribed by the healthcare provider.

Missed Dose

If a dose of BRUKINSA is missed, it should be taken as soon as possible on the same day with a return to the normal schedule the following day.

2.2 Dosage Modification for Use in Hepatic Impairment

The recommended dosage of BRUKINSA for patients with severe hepatic impairment (Child-Pugh class C) is 80 mg orally twice daily; no dosage modification is recommended for patients with mild or moderate hepatic impairment (Child-Pugh class A or B) [see Use in Specific Populations (8.7) and Clinical Pharmacology (12.3)].

2.3 Dosage Modifications for Drug Interactions

Recommended dosage modifications of BRUKINSA for drug interactions are provided in Table 1 [see Drug Interactions (7.1)].

Table 1: Dosage Modifications for Use with CYP3A Inhibitors or Inducers
Coadministered Drug | Recommended BRUKINSA Dosage (Starting Dose: 160 mg twice daily or 320 mg once daily)
Clarithromycin 250 mg twice daily [Since clarithromycin 250 mg twice daily acts as a moderate CYP3A inhibitor, it is recommended that patients be administered clarithromycin 250 mg twice daily with 80 mg BRUKINSA twice daily [see Clinical Pharmacology (12.3)].] | 80 mg twice daily [Modify or interrupt zanubrutinib dose as recommended for adverse reactions [see Dosage and Administration (2.4)].]
Clarithromycin 500 mg twice daily | 80 mg once daily
Posaconazole suspension 100 mg once daily | 80 mg twice daily
Posaconazole suspension dosage higher than 100 mg once daily Posaconazole delayed-release tablets 300 mg once daily Posaconazole intravenous 300 mg once daily | 80 mg once daily
Other strong CYP3A inhibitor | 80 mg once daily
Moderate CYP3A inhibitor | 80 mg twice daily
Strong CYP3A inducer | Avoid concomitant use.
Moderate CYP3A inducer | Avoid concomitant use. If these inducers cannot be avoided, increase BRUKINSA dose to 320 mg twice daily.

After discontinuation of a CYP3A inhibitor or moderate CYP3A inducer, resume previous dose of BRUKINSA [see Dosage and Administration (2.1, 2.2) and Drug Interactions (7.1)].

2.4 Dosage Modifications for Adverse Reactions

Recommended dosage modifications of BRUKINSA for Grade 3 or higher adverse reactions are provided in Table 2.

Table 2: Recommended Dosage Modifications for Adverse Reaction
Adverse Reaction | Adverse Reaction Occurrence | Dosage Modification (Starting Dose: 160 mg twice daily or 320 mg once daily)
Hematological toxicities [see Warnings and Precautions (5.3)]
Grade 3 or Grade 4 febrile neutropenia Platelet count decreased to 25,000-50,000/mm^3 with significant bleeding Neutrophil count decreased to <500/mm^3 (lasting more than 10 consecutive days) Platelet count decreased to <25,000/mm^3 (lasting more than 10 consecutive days) | First | Interrupt BRUKINSA Once toxicity has resolved to Grade 1 or lower or baseline: Resume at 160 mg twice daily or 320 mg once daily.
Grade 3 or Grade 4 febrile neutropenia Platelet count decreased to 25,000-50,000/mm^3 with significant bleeding Neutrophil count decreased to <500/mm^3 (lasting more than 10 consecutive days) Platelet count decreased to <25,000/mm^3 (lasting more than 10 consecutive days) | Second | Interrupt BRUKINSA Once toxicity has resolved to Grade 1 or lower or baseline: Resume at 80 mg twice daily or 160 mg once daily.
Grade 3 or Grade 4 febrile neutropenia Platelet count decreased to 25,000-50,000/mm^3 with significant bleeding Neutrophil count decreased to <500/mm^3 (lasting more than 10 consecutive days) Platelet count decreased to <25,000/mm^3 (lasting more than 10 consecutive days) | Third | Interrupt BRUKINSA Once toxicity has resolved to Grade 1 or lower or baseline: Resume at 80 mg once daily.
Grade 3 or Grade 4 febrile neutropenia Platelet count decreased to 25,000-50,000/mm^3 with significant bleeding Neutrophil count decreased to <500/mm^3 (lasting more than 10 consecutive days) Platelet count decreased to <25,000/mm^3 (lasting more than 10 consecutive days) | Fourth | Discontinue BRUKINSA
Nonhematological toxicities [see Warnings and Precautions (5.5) and Adverse Reactions (6.1)]
Severe or life-threatening nonhematological toxicities [Evaluate the benefit-risk before resuming treatment at the same dosage for Grade 4 nonhematological toxicity.] | First | Interrupt BRUKINSA Once toxicity has resolved to Grade 1 or lower or baseline: Resume at 160 mg twice daily or 320 mg once daily.
Severe or life-threatening nonhematological toxicities [Evaluate the benefit-risk before resuming treatment at the same dosage for Grade 4 nonhematological toxicity.] | Second | Interrupt BRUKINSA Once toxicity has resolved to Grade 1 or lower or baseline: Resume at 80 mg twice daily or 160 mg once daily.
Severe or life-threatening nonhematological toxicities [Evaluate the benefit-risk before resuming treatment at the same dosage for Grade 4 nonhematological toxicity.] | Third | Interrupt BRUKINSA Once toxicity has resolved to Grade 1 or lower or baseline: Resume at 80 mg once daily.
Severe or life-threatening nonhematological toxicities [Evaluate the benefit-risk before resuming treatment at the same dosage for Grade 4 nonhematological toxicity.] | Fourth | Discontinue BRUKINSA

Asymptomatic lymphocytosis in CLL and MCL should not be regarded as an adverse reaction, and these patients should continue taking BRUKINSA.

Refer to the obinutuzumab prescribing information for management of obinutuzumab toxicities.

3 DOSAGE FORMS AND STRENGTHS

Capsules: Each 80 mg capsule is a size 0, white to off-white opaque capsule marked with "ZANU 80" in black ink.

Tablets: 160 mg, blue, oval, film-coated tablets debossed with "zanu" on one side and functional scoring on the other side.

4 CONTRAINDICATIONS

None.

5 WARNINGS AND PRECAUTIONS

5.1 Hemorrhage

Fatal and serious hemorrhage has occurred in patients with hematological malignancies treated with BRUKINSA. Grade 3 or higher hemorrhage including intracranial and gastrointestinal hemorrhage, hematuria, and hemothorax was reported in 3.8% of patients treated with BRUKINSA in clinical trials, with fatalities occurring in 0.2% of patients. Bleeding of any grade, excluding purpura and petechiae, occurred in 32% of patients.

Bleeding has occurred in patients with and without concomitant antiplatelet or anticoagulation therapy. Coadministration of BRUKINSA with antiplatelet or anticoagulant medications may further increase the risk of hemorrhage.

Monitor for signs and symptoms of bleeding. Discontinue BRUKINSA if intracranial hemorrhage of any grade occurs. Consider the benefit-risk of withholding BRUKINSA for 3-7 days before and after surgery depending upon the type of surgery and the risk of bleeding.

5.2 Infections

Fatal and serious infections (including bacterial, viral, or fungal infections) and opportunistic infections have occurred in patients with hematological malignancies treated with BRUKINSA. Grade 3 or higher infections occurred in 26% of patients, most commonly pneumonia (7.9%), with fatal infections occurring in 3.2% of patients. Infections due to hepatitis B virus (HBV) reactivation have occurred.

Consider prophylaxis for herpes simplex virus, pneumocystis jirovecii pneumonia, and other infections according to standard of care in patients who are at increased risk for infections. Monitor and evaluate patients for fever or other signs and symptoms of infection and treat appropriately.

5.3 Cytopenias

Grade 3 or 4 cytopenias, including neutropenia (21%), thrombocytopenia (8%), and anemia (8%) based on laboratory measurements, developed in patients treated with BRUKINSA [see Adverse Reactions (6.1)]. Grade 4 neutropenia occurred in 10% of patients, and Grade 4 thrombocytopenia occurred in 2.5% of patients.

Monitor complete blood counts regularly during treatment and interrupt treatment, reduce the dose, or discontinue treatment as warranted [see Dosage and Administration (2.4)]. Treat using growth factor or transfusions, as needed.

5.4 Second Primary Malignancies

Second primary malignancies, including non-skin carcinoma, have occurred in 14% of patients treated with BRUKINSA. The most frequent second primary malignancy was non-melanoma skin cancers (8%), followed by other solid tumors in 7% of the patients (including melanoma in 1% of patients) and hematologic malignancies (0.7%). Advise patients to use sun protection and monitor patients for the development of second primary malignancies.

5.5 Cardiac Arrhythmias

Serious cardiac arrhythmias have occurred in patients treated with BRUKINSA. Atrial fibrillation and atrial flutter were reported in 4.4% of patients treated with BRUKINSA, including Grade 3 or higher cases in 1.9% of patients. Patients with cardiac risk factors, hypertension, and acute infections may be at increased risk. Grade 3 or higher ventricular arrhythmias were reported in 0.3% of patients.

Monitor for signs and symptoms of cardiac arrhythmias (e.g., palpitations, dizziness, syncope, dyspnea, chest discomfort), manage appropriately [see Dosage and Administration (2.4)], and consider the risks and benefits of continued BRUKINSA treatment.

5.6 Hepatotoxicity, Including Drug-Induced Liver Injury

Hepatotoxicity, including severe, life-threatening, and potentially fatal cases of drug-induced liver injury (DILI), has occurred in patients treated with Bruton tyrosine kinase inhibitors, including BRUKINSA.

Evaluate bilirubin and transaminases at baseline and throughout treatment with BRUKINSA. For patients who develop abnormal liver tests after BRUKINSA, monitor more frequently for liver test abnormalities and clinical signs and symptoms of hepatic toxicity. If DILI is suspected, withhold BRUKINSA. Upon confirmation of DILI, discontinue BRUKINSA.

5.7 Embryo-Fetal Toxicity

Based on findings in animals, BRUKINSA can cause fetal harm when administered to a pregnant woman. Administration of zanubrutinib to pregnant rats during the period of organogenesis caused embryo-fetal toxicity, including malformations at exposures that were 5 times higher than those reported in patients at the recommended dose of 160 mg twice daily. Advise women to avoid becoming pregnant while taking BRUKINSA and for 1 week after the last dose. Advise men to avoid fathering a child during treatment and for 1 week after the last dose. If this drug is used during pregnancy, or if the patient becomes pregnant while taking this drug, the patient should be apprised of the potential hazard to a fetus [see Use in Specific Populations (8.1)].

6 ADVERSE REACTIONS

The following clinically significant adverse reactions are discussed in more detail in other sections of the labeling:

- Hemorrhage [see Warnings and Precautions (5.1)]
- Infections [see Warnings and Precautions (5.2)]
- Cytopenias [see Warnings and Precautions (5.3)]
- Second Primary Malignancies [see Warnings and Precautions (5.4)]
- Cardiac Arrhythmias [see Warnings and Precautions (5.5)]
- Hepatotoxicity, including DILI [see Warnings and Precautions (5.6)]

6.1 Clinical Trials Experience

Because clinical trials are conducted under widely varying conditions, adverse reaction rates observed in the clinical trials of a drug cannot be directly compared to rates in the clinical trials of another drug and may not reflect the rates observed in practice.

The data in the WARNINGS AND PRECAUTIONS reflect exposure to BRUKINSA in nine monotherapy and 2 combination clinical trials, administered at 160 mg twice daily in 1608 patients and at 320 mg once daily in 121 patients. Among these 1729 patients, the median duration of exposure was 27.6 months, 78% of patients were exposed for at least 12 months, and 60% of patients were exposed for at least 24 months.

In this pooled safety population, the most common adverse reactions (≥30%), including laboratory abnormalities, were neutrophil count decreased (51%), platelet count decreased (41%), upper respiratory tract infection (38%), hemorrhage (32%), and musculoskeletal pain (31%).

Mantle Cell Lymphoma (MCL)

The safety of BRUKINSA was evaluated in 118 patients with MCL who received at least one prior therapy in two single-arm clinical trials, BGB-3111-206 [NCT03206970] and BGB-3111-AU-003 [NCT02343120] [see Clinical Studies (14.1)]. The median age of patients who received BRUKINSA in studies BGB-3111-206 and BGB-3111-AU-003 was 62 years (range: 34 to 86), 75% were male, 75% were Asian, 21% were White, and 94% had an ECOG performance status of 0 to 1. Patients had a median of 2 prior lines of therapy (range: 1 to 4). The BGB-3111-206 trial required a platelet count ≥75 × 10^9/L and an absolute neutrophil count ≥1 × 10^9/L independent of growth factor support, hepatic enzymes ≤2.5 × upper limit of normal, total bilirubin ≤1.5 × ULN. The BGB-3111-AU-003 trial required a platelet count ≥50 × 10^9/L and an absolute neutrophil count ≥1 × 10^9/L independent of growth factor support, hepatic enzymes ≤3 × upper limit of normal, total bilirubin ≤1.5 × ULN. Both trials required a creatinine clearance (CLcr) ≥30 mL/min. Both trials excluded patients with prior allogeneic hematopoietic stem cell transplant, exposure to a BTK inhibitor, known infection with HIV, and serologic evidence of active hepatitis B or hepatitis C infection, and patients requiring strong CYP3A inhibitors or strong CYP3A inducers. Patients received BRUKINSA 160 mg twice daily or 320 mg once daily. Among patients receiving BRUKINSA, 79% were exposed for 6 months or longer, and 68% were exposed for greater than one year.

Fatal adverse reactions within 30 days of the last dose of BRUKINSA occurred in 8 (7%) of 118 patients with MCL. Fatal cases included pneumonia in 2 patients and cerebral hemorrhage in one patient.

Serious adverse reactions were reported in 36 patients (31%). The most frequent serious adverse reactions that occurred were pneumonia (11%) and hemorrhage (5%).

Of the 118 patients with MCL treated with BRUKINSA, 8 (7%) patients discontinued treatment due to adverse reactions in the trials. The most frequent adverse reaction leading to treatment discontinuation was pneumonia (3.4%). One (0.8%) patient experienced an adverse reaction leading to dose reduction (hepatitis B).

Table 3 summarizes the adverse reactions in BGB-3111-206 and BGB-3111-AU-003.

Table 3: Adverse Reactions (≥10%) in Patients Receiving BRUKINSA in BGB-3111-206 and BGB-3111-AU-003 Trials
Body System | Adverse Reaction | Percent of Patients (N=118)
Body System | Adverse Reaction | All Grades % | Grade 3 or Higher %
Infections and infestations | Upper respiratory tract infection [Upper respiratory tract infection includes upper respiratory tract infection, upper respiratory tract infection viral.] | 39 | 0
 | Pneumonia [Pneumonia includes pneumonia, pneumonia fungal, pneumonia cryptococcal, pneumonia streptococcal, atypical pneumonia, lung infection, lower respiratory tract infection, lower respiratory tract infection bacterial, lower respiratory tract infection viral.] | 15 | 10 [Includes fatal adverse reaction.]
 | Urinary tract infection | 11 | 0.8
Skin and subcutaneous tissue disorders | Rash [Rash includes all related terms containing rash.] | 36 | 0
Skin and subcutaneous tissue disorders | Bruising [Bruising includes all related terms containing bruise, bruising, contusion, ecchymosis.] | 14 | 0
Gastrointestinal disorders | Diarrhea | 23 | 0.8
 | Constipation | 13 | 0
Vascular disorders | Hypertension | 12 | 3.4
 | Hemorrhage [Hemorrhage includes all related terms containing hemorrhage, hematoma.] | 11 | 3.4
Musculoskeletal and connective tissue disorders | Musculoskeletal pain [Musculoskeletal pain includes musculoskeletal pain, musculoskeletal discomfort, myalgia, back pain, arthralgia, arthritis.] | 14 | 3.4
Respiratory, thoracic, and mediastinal disorders | Cough | 12 | 0

Other clinically significant adverse reactions that occurred in <10% of patients with mantle cell lymphoma include major hemorrhage (defined as ≥ Grade 3 hemorrhage or CNS hemorrhage of any grade) (5%) and headache (4.2%).

Table 4: Selected Laboratory Abnormalities [Based on laboratory measurements.] (>20%) in Patients with MCL in Studies BGB-3111-206 and BGB-3111-AU-003
Laboratory Parameter | Percent of Patients (N=118)
Laboratory Parameter | All Grades (%) | Grade 3 or 4 (%)
Hematologic abnormalities
Neutrophils decreased | 45 | 20
Lymphocytosis [Asymptomatic lymphocytosis is a known effect of BTK inhibition.] | 41 | 16
Platelets decreased | 40 | 7
Hemoglobin decreased | 27 | 6
Chemistry abnormalities
Blood uric acid increased | 29 | 2.6
ALT increased | 28 | 0.9
Bilirubin increased | 24 | 0.9

Waldenström's Macroglobulinemia (WM)

The safety of BRUKINSA was investigated in two cohorts of Study BGB-3111-302 (ASPEN). Cohort 1 included 199 patients with MYD88 mutation (MYD88MUT) WM, randomized to and treated with either BRUKINSA (101 patients) or ibrutinib (98 patients). The trial also included a non-randomized arm, Cohort 2, with 26 wild type MYD88 (MYD88WT) WM patients and 2 patients with unknown MYD88 status [see Clinical Studies (14.2)].

Among patients who received BRUKINSA, 93% were exposed for 6 months or longer, and 89% were exposed for greater than 1 year.

In Cohort 1 of the ASPEN study safety population (N=101), the median age of patients who received BRUKINSA was 70 years (45-87 years old); 67% were male, 86% were White, 4% were Asian, and 10% were not reported (unknown race). In Cohort 2 of the ASPEN study safety population (N=28), the median age of patients who received BRUKINSA was 72 (39-87 years old); 50% were male, 96% were White, and 4% were not reported (unknown race).

In Cohort 1, serious adverse reactions occurred in 44% of patients who received BRUKINSA. Serious adverse reactions in >2% of patients included influenza (3%), pneumonia (4%), neutropenia and neutrophil count decreased (3%), hemorrhage (4%), pyrexia (3%), and febrile neutropenia (3%). In Cohort 2, serious adverse reactions occurred in 39% of patients. Serious adverse reactions in >2 patients included pneumonia (14%).

Permanent discontinuation of BRUKINSA due to an adverse reaction occurred in 2% of patients in Cohort 1 and included hemorrhage (1 patient), neutropenia and neutrophil count decreased (1 patient); in Cohort 2, permanent discontinuation of BRUKINSA due to an adverse reaction occurred in 7% of patients and included subdural hemorrhage (1 patient) and diarrhea (1 patient).

Dosage interruptions of BRUKINSA due to an adverse reaction occurred in 32% of patients in Cohort 1 and in 29% in Cohort 2. Adverse reactions which required dosage interruption in >2% of patients included neutropenia, vomiting, hemorrhage, thrombocytopenia, and pneumonia in Cohort 1. Adverse reactions leading to dosage interruption in >2 patients in Cohort 2 included pneumonia and pyrexia.

Dose reductions of BRUKINSA due to an adverse reaction occurred in 11% of patients in Cohort 1 and in 7% in Cohort 2. Adverse reactions which required dose reductions in >2% of patients included neutropenia in Cohort 1. Adverse reaction leading to dose reduction occurred in 2 patients in Cohort 2 (each with one event: diarrhea and pneumonia).

Table 5 summarizes the adverse reactions in Cohort 1 in ASPEN.

Table 5: Adverse Reactions (≥10%) Occurring in Patients with WM Who Received BRUKINSA in Cohort 1
Body System | Adverse Reaction | BRUKINSA (N=101) |  | Ibrutinib (N=98)
Body System | Adverse Reaction | All Grades (%) | Grade 3 or 4 (%) | All Grades (%) | Grade 3 or 4 (%)
Body System | Adverse Reaction | Infections and infestations | Grade 3 or 4 (%) | Upper respiratory tract infection [Upper respiratory tract infection includes upper respiratory tract infection, laryngitis, nasopharyngitis, sinusitis, rhinitis, viral upper respiratory tract infection, pharyngitis, rhinovirus infection, upper respiratory tract congestion.] | Grade 3 or 4 (%) | 44 | 0 | 40 | 2
Pneumonia [Pneumonia includes lower respiratory tract infection, lung infiltration, pneumonia, pneumonia aspiration, pneumonia viral.] | 12 | Infections and infestations | 4 | 26 | 10
Urinary tract infection | 11 | Infections and infestations | 0 | 13 | 2
Gastrointestinal disorders | Diarrhea | 22 | 3 | 34 | 2
Gastrointestinal disorders | Nausea | 18 | 0 | 13 | 1
Gastrointestinal disorders | Constipation | 16 | 0 | 7 | 0
Gastrointestinal disorders | Vomiting | 12 | 0 | 14 | 1
General disorders | Fatigue [Fatigue includes asthenia, fatigue, lethargy.] | 31 | 1 | 25 | 1
General disorders | Pyrexia | 16 | 4 | 13 | 2
General disorders | Edema peripheral | 12 | 0 | 20 | 0
Skin and subcutaneous tissue disorders | Bruising [Bruising includes all related terms containing bruise, contusion, or ecchymosis.] | 20 | 0 | 34 | 0
Skin and subcutaneous tissue disorders | Rash [Rash includes all related terms rash, maculo-papular rash, erythema, rash erythematous, drug eruption, dermatitis allergic, dermatitis atopic, rash pruritic, dermatitis, photodermatoses, dermatitis acneiform, stasis dermatitis, vasculitic rash, eyelid rash, urticaria, skin toxicity.] | 29 | 0 | 32 | 0
Skin and subcutaneous tissue disorders | Pruritus | 11 | 1 | 6 | 0
Musculoskeletal and connective tissue disorders | Musculoskeletal pain [Musculoskeletal pain includes back pain, arthralgia, pain in extremity, musculoskeletal pain, myalgia, bone pain, spinal pain, musculoskeletal chest pain, neck pain, arthritis, musculoskeletal discomfort.] | 45 | 9 | 39 | 1
Musculoskeletal and connective tissue disorders | Muscle spasms | 10 | 0 | 28 | 1
Nervous system disorders | Headache | 18 | 1 | 14 | 1
Nervous system disorders | Dizziness | 13 | 1 | 12 | 0
Respiratory, thoracic, and mediastinal disorders | Cough | 16 | 0 | 18 | 0
Respiratory, thoracic, and mediastinal disorders | Dyspnea | 14 | 0 | 7 | 0
Vascular disorders | Hemorrhage [Hemorrhage includes epistaxis, hematuria, conjunctival hemorrhage, hematoma, rectal hemorrhage, periorbital hemorrhage, mouth hemorrhage, post procedural hemorrhage, hemoptysis, skin hemorrhage, hemorrhoidal hemorrhage, ear hemorrhage, eye hemorrhage, hemorrhagic diathesis, periorbital hematoma, subdural hemorrhage, wound hemorrhage, gastric hemorrhage, lower gastrointestinal hemorrhage, spontaneous hematoma, traumatic hematoma, traumatic intracranial hemorrhage, tumor hemorrhage, retinal hemorrhage, hematochezia, diarrhea hemorrhagic, hemorrhage, melena, post-procedural hematoma, subdural hematoma, anal hemorrhage, hemorrhagic disorder, pericardial hemorrhage, postmenopausal hemorrhage, stoma site hemorrhage, subarachnoid hemorrhage.] | 42 | 4 | 43 | 9
Vascular disorders | Hypertension | 14 | 9 | 19 | 14

Clinically relevant adverse reactions in <10% of patients who received BRUKINSA included localized infection, atrial fibrillation or atrial flutter, and hematuria.

Table 6 summarizes the laboratory abnormalities in ASPEN.

Table 6: Select Laboratory Abnormalities [Based on laboratory measurements.] (≥20%) that Worsened from Baseline in Patients with WM Who Received BRUKINSA in Cohort 1
Laboratory Abnormality | BRUKINSA [The denominator used to calculate the rate varied from 86 to 101 based on the number of patients with a baseline value and at least one post-treatment value.] |  | Ibrutinib
Laboratory Abnormality | All Grades (%) | Grade 3 or 4 (%) | All Grades (%) | Grade 3 or 4 (%)
Hematologic abnormalities
Neutrophils decreased | 50 | 24 | 34 | 9
Platelets decreased | 35 | 8 | 39 | 5
Hemoglobin decreased | 20 | 7 | 20 | 7
Chemistry abnormalities
Glucose increased | 45 | 2.3 | 33 | 2.3
Creatinine increased | 31 | 1 | 21 | 1
Calcium decreased | 27 | 2 | 26 | 0
Potassium increased | 24 | 2 | 12 | 0
Phosphate decreased | 20 | 3.1 | 18 | 0
Urate increased | 16 | 3.2 | 34 | 6
Bilirubin increased | 12 | 1 | 33 | 1

Marginal Zone Lymphoma

The safety of BRUKINSA was evaluated in 88 patients with previously treated MZL in two single-arm clinical studies, BGB-3111-214 and BGB-3111-AU-003 [see Clinical Studies (14.3)]. The trials required an absolute neutrophil count ≥1 × 10^9/L, platelet count ≥50 or ≥75 × 10^9/L and adequate hepatic function and excluded patients requiring a strong CYP3A inhibitor or inducer. Patients received BRUKINSA 160 mg twice daily (97%) or 320 mg once daily (3%). The median age in both studies combined was 70 years (range: 37 to 95), 52% were male, 64% were White, and 19% were Asian. Most patients (92%) had an ECOG performance status of 0 to 1. Eighty percent received BRUKINSA for 6 months or longer, and 67% received treatment for more than one year.

Two fatal adverse reactions (2.3%) occurred within 30 days of the last dose of BRUKINSA, including myocardial infarction and a Covid-19–related death.

Serious adverse reactions occurred in 40% of patients. The most frequent serious adverse reactions were pyrexia (8%) and pneumonia (7%).

Adverse reactions lead to treatment discontinuation in 6% of patients, dose reduction in 2.3%, and dose interruption in 34%. The leading cause of dose modification was respiratory tract infections (13%).

Table 7 summarizes selected adverse reactions in BGB-3111-214 and BGB-3111-AU-003.

Table 7: Adverse Reactions Occurring in ≥10% Patients with MZL Who Received BRUKINSA
Body System | Adverse Reaction | BRUKINSA (N=88)
Body System | Adverse Reaction | All Grades (%) | Grade 3 or 4 (%)
Infections and infestations | Upper respiratory tract infection [Upper respiratory tract infection includes upper respiratory tract infection, nasopharyngitis, sinusitis, tonsillitis, rhinitis, viral upper respiratory tract infection.] | 26 | 3.4
 | Urinary tract infection [Urinary tract infection includes urinary tract infection, cystitis, Escherichia urinary tract infection, pyelonephritis, cystitis.] | 11 | 2.3
 | Pneumonia [Pneumonia includes COVID-19 pneumonia, pneumonia, bronchopulmonary aspergillosis, lower respiratory tract infection, organizing pneumonia.] , [Includes 2 fatalities from COVID-19 pneumonia.] | 10 | 6
Gastrointestinal disorders | Diarrhea [Diarrhea includes diarrhea and diarrhea hemorrhagic.] | 25 | 3.4
 | Abdominal pain [Abdominal pain includes abdominal pain, abdominal pain upper, abdominal discomfort.] | 14 | 2.3
 | Nausea | 13 | 0
Skin and subcutaneous tissue disorders | Bruising [Bruising includes contusion, ecchymosis, increased tendency to bruise, post procedural contusion.] | 24 | 0
Skin and subcutaneous tissue disorders | Rash [Rash includes rash, rash maculo-papular, rash pruritic, dermatitis, dermatitis allergic, dermatitis atopic, dermatitis contact, drug reaction with eosinophilia and systemic symptoms, erythema, photosensitivity reaction, rash erythematous, rash papular, seborrheic dermatitis.] | 21 | 0
Musculoskeletal and connective tissue disorders | Musculoskeletal pain [Musculoskeletal pain includes back pain, arthralgia, musculoskeletal pain, myalgia, pain in extremity, musculoskeletal chest pain, bone pain, musculoskeletal discomfort, neck pain.] | 27 | 1.1
Vascular disorders | Hemorrhage [Hemorrhage includes epistaxis, hematuria, hemorrhoidal hemorrhage, hematoma, hemoptysis, conjunctival hemorrhage, diarrhea hemorrhagic, hemorrhage urinary tract, mouth hemorrhage, pulmonary hematoma, subcutaneous hematoma, gingival bleeding, melena, upper gastrointestinal hemorrhage.] | 23 | 1.1
General disorders | Fatigue [Fatigue includes fatigue, lethargy, asthenia.] | 21 | 2.3
Respiratory, thoracic, and mediastinal disorders | Cough [Cough includes cough and productive cough.] | 10 | 0

Clinically relevant adverse reactions in <10% of patients who received BRUKINSA included peripheral neuropathy, second primary malignancies, dizziness, edema, headache, petechiae, purpura, and atrial fibrillation or flutter.

Table 8 summarizes select laboratory abnormalities.

Table 8: Select Laboratory Abnormalities (≥20%) that Worsened from Baseline in Patients with MZL
Laboratory Abnormality [The denominator used to calculate the rate varied from 87 to 88 based on the number of patients with a baseline value and at least one post-treatment value.] | BRUKINSA
Laboratory Abnormality [The denominator used to calculate the rate varied from 87 to 88 based on the number of patients with a baseline value and at least one post-treatment value.] | All Grades (%) | Grade 3 or 4 (%)
Hematologic abnormalities
Neutrophils decreased | 43 | 15
Platelets decreased | 33 | 10
Lymphocytes decreased | 32 | 8
Hemoglobin decreased | 26 | 6
Chemistry abnormalities
Glucose increased | 54 | 4.6
Creatinine increased | 34 | 1.1
Phosphate decreased | 27 | 2.3
Calcium decreased | 23 | 0
ALT increased | 22 | 1.1

Chronic Lymphocytic Leukemia or Small Lymphocytic Lymphoma

The safety data described below reflect exposure to BRUKINSA (160 mg twice daily) in 675 patients with CLL from two randomized controlled clinical trials [see Clinical Studies (14.4)]. The trials required patients to be unsuitable for fludarabine, cyclophosphamide, and rituximab (FCR) therapy defined as age ≥65 years, or age 18 to <65 years with either a total Cumulative Illness Rating Scale (CIRS) >6, CLcr 30 to 69 mL/min, or history of serious or frequent infections. The trial excluded patients with AST or ALT ≥2 times the upper limit of normal (ULN) or bilirubin ≥3 times (ULN) and patients requiring a strong CYP3A inhibitor or inducer.

SEQUOIA

The safety of BRUKINSA monotherapy in patients with previously untreated CLL/SLL was evaluated in a randomized, multicenter, open-label, actively controlled trial [see Clinical Studies (14.4)]. Patients without deletion of chromosome 17p13.1 (17p deletion) (Cohort 1) received either BRUKINSA 160 mg twice daily until disease progression or unacceptable toxicity (n=240) or bendamustine plus rituximab (BR) for 6 cycles (n=227). Bendamustine was dosed at 90 mg/m^2/day intravenously on the first 2 days of each cycle, and rituximab was dosed at 375 mg/m^2 on day 1 of Cycle 1 and 500 mg/m^2 on day 1 of Cycles 2 to 6.

Additionally, the same BRUKINSA regimen was evaluated in 111 patients with previously untreated CLL/SLL with 17p deletion in a non-randomized single arm (Cohort 2).

Randomized Cohort: Previously Untreated CLL/SLL without 17p Deletion

In patients with previously untreated CLL/SLL without 17p deletion, the median age was 70, 62% were male, 89% were White, 2% were Asian, and 2% were Black. Most patients (93%) had an ECOG performance status of 0 to 1.

The median duration of exposure to BRUKINSA was 26 months, with 71% exposed for more than 2 years.

Serious adverse reactions occurred in 36% of patients who received BRUKINSA. Serious adverse reactions that occurred in ≥5% of patients were COVID-19, pneumonia, and second primary malignancy (5% each). Fatal adverse reactions occurred in 11 (4.6%) patients with the leading cause of death being COVID-19 (2.1%).

Adverse reactions led to permanent discontinuation of BRUKINSA in 8% of patients, dose reduction in 8%, and dose interruption in 46%. The most common adverse reactions leading to permanent discontinuation were second primary malignancy and COVID-19. The leading causes of dose modification (≥5% of all patients) were respiratory infections (COVID-19, pneumonia) and hemorrhage.

Table 9 summarizes select adverse reactions in this randomized cohort.

Table 9: Adverse Reactions in ≥10% Patients with Previously Untreated CLL/SLL without 17p Deletion in SEQUOIA
 | CLL/SLL without 17p deletion
 | BRUKINSA (N=240) |  | BR (N=227)
System Organ Class Preferred Term | All Grades (%) | Grade 3 or 4 (%) | All Grades (%) | Grade 3 or 4 (%)
Musculoskeletal and connective tissue disorders
Musculoskeletal pain [Musculoskeletal pain: musculoskeletal pain, arthralgia, back pain, pain in extremity, myalgia, neck pain, spinal pain, musculoskeletal discomfort, bone pain.] | 33 | 1.7 | 17 | 0.4
Infections and infestations
Upper respiratory tract infection [Upper respiratory tract infection: upper respiratory tract infection, nasopharyngitis, sinusitis, rhinitis, pharyngitis, upper respiratory tract congestion, laryngitis, tonsillitis and upper respiratory tract inflammation, and related terms.] | 28 | 1.3 | 15 | 0.9
Pneumonia [Pneumonia: pneumonia, COVID-19 pneumonia, lower respiratory tract infection, lung infiltration, and related terms including specific types of infection.] | 13 [Includes 3 fatal outcomes.] | 5 | 8 [Includes 2 fatal outcomes.] | 4
Vascular disorders
Hemorrhage [Hemorrhage: all terms containing hematoma, hemorrhage, hemorrhagic, and related terms indicative of bleeding.] | 27 | 4 | 4 | 0.4
Hypertension [Includes multiple similar adverse reaction terms.] | 14 | 7 | 5 | 2.6
Skin and subcutaneous tissue disorders
Rash [Rash: Rash, dermatitis, drug eruption, and related terms.] | 24 | 1.3 | 30 | 5
Bruising [Bruising: all terms containing bruise, bruising, contusion, or ecchymosis.] | 24 | 0 | 2.6 | 0
Respiratory, thoracic, and mediastinal disorders
Cough | 15 | 0 | 10 | 0
Gastrointestinal disorders
Diarrhea | 14 | 0.8 | 12 | 0.9
Constipation | 10 | 0.4 | 18 | 0
Nausea | 10 | 0 | 33 | 1.3
General disorders
Fatigue [Fatigue: fatigue, asthenia, and lethargy.] | 14 | 1.3 | 21 | 1.8
Neoplasms
Second primary malignancy [Second primary malignancy: includes non-melanoma skin cancer, malignant solid tumors (including lung, renal, genitourinary, breast, ovarian, and rectal), and chronic myeloid leukemia.] | 13 | 6 | 1.3 | 0.4
Nervous system disorders
Headache | 12 | 0 | 8 | 0
Dizziness [Dizziness: dizziness and vertigo.] | 11 | 0.8 | 5 | 0

Other clinically significant adverse reactions occurring in <10% of BRUKINSA recipients in this cohort included COVID-19 (9%), edema (8%), abdominal pain (8%), urinary tract infection (7%), and atrial fibrillation or flutter (3.3%).

Table 10 summarizes select laboratory abnormalities in this cohort.

Table 10: Select Laboratory Abnormalities (≥20%) that Worsened from Baseline in Patients with Previously Untreated CLL/SLL without 17p Deletion in SEQUOIA
Laboratory Abnormality [The denominator used to calculate the rate was 239 in the BRUKINSA arm and 227 in the BR arm, based on the number of patients with a baseline value and at least one post-treatment value. Grading is based on NCI CTCAE criteria.] | BRUKINSA |  | BR
Laboratory Abnormality [The denominator used to calculate the rate was 239 in the BRUKINSA arm and 227 in the BR arm, based on the number of patients with a baseline value and at least one post-treatment value. Grading is based on NCI CTCAE criteria.] | All Grades (%) | Grade 3 or 4 (%) | All Grades (%) | Grade 3 or 4 (%)
Hematologic abnormalities
Neutrophils decreased | 37 | 15 | 80 | 53
Hemoglobin decreased | 29 | 2.5 | 66 | 8
Platelets decreased | 27 | 1.7 | 61 | 11
Leukocytes increased | 21 [Lymphocytes increased in 15%.] | 21 | 0.4 | 0.4
Chemistry abnormalities
Glucose increased [Nonfasting conditions.] | 55 | 7 | 67 | 10
Creatinine increased | 22 | 0.8 | 18 | 0.4
Magnesium increased | 22 | 0 | 14 | 0.4
Alanine aminotransferase increased | 21 | 2.1 | 23 | 2.2

Single-Arm Cohort: Previously Untreated CLL/SLL and 17p Deletion

In 111 patients with previously untreated, 17p del CLL/SLL, the median age was 70, 71% were male, 95% were White, and 1% were Asian. Most patients (87%) had an ECOG performance status of 0 to 1. The median duration of exposure to BRUKINSA was 30 months.

Fatal adverse reactions occurred in 3 (2.7%) patients, including pneumonia, renal insufficiency, and aortic dissection (1 patient each).

Serious adverse reactions occurred in 41% of patients treated with BRUKINSA. Serious adverse reactions reported in ≥5% of patients were pneumonia (8%) and second primary malignancy (7%).

Adverse reactions led to treatment discontinuation in 5% of patients, dose reduction in 5%, and dose interruption in 51%. The leading causes of dose modification (≥5% of all patients) were pneumonia, neutropenia, second primary malignancy, and diarrhea.

Table 11 summarizes select adverse reactions in this cohort.

Table 11: Adverse Reactions in ≥10% of Patients with Previously Untreated CLL/SLL and 17p Deletion in SEQUOIA
 | CLL/SLL with 17p Deletion
 | BRUKINSA (N=111)
System Organ Class Preferred Term | All Grades (%) | Grade 3 or 4 (%)
Infections and infestations
Upper respiratory tract infection [Upper respiratory tract infection: upper respiratory tract infection, nasopharyngitis, sinusitis, rhinitis, pharyngitis, upper respiratory tract congestion, upper respiratory tract inflammation, viral upper respiratory tract infection, and related terms.] | 38 | 0
Pneumonia [Pneumonia: pneumonia, COVID-19 pneumonia, lower respiratory tract infection, and related terms including specific types of infection.] | 20 [Includes 1 fatal outcome.] | 8
Musculoskeletal and connective tissue disorders
Musculoskeletal pain [Musculoskeletal pain: musculoskeletal pain, arthralgia, back pain, pain in extremity, myalgia, neck pain, bone pain.] | 38 | 2.7
Skin and subcutaneous tissue disorders
Rash [Rash: Rash, dermatitis, toxic skin eruption, and related terms.] | 28 | 0
Bruising [Bruising: all terms containing bruise, bruising, contusion, or ecchymosis.] | 26 | 0.9
Vascular disorders
Hemorrhage [Hemorrhage: all terms containing hematoma, hemorrhage, hemorrhagic, and related terms indicative of bleeding.] | 28 | 4.5
Hypertension | 11 | 5.4
Neoplasms
Second primary malignancy [Second primary malignancy: includes non-melanoma skin cancer, malignant solid tumors (including bladder, lung, renal, breast, prostate, ovarian, pelvis, and ureter), and malignant melanoma.] | 22 [Includes non-melanoma skin cancer in 13%.] | 6
Gastrointestinal disorders
Diarrhea | 18 | 0.9
Nausea | 16 | 0
Constipation | 15 | 0
Abdominal pain | 12 | 1.8
Respiratory, thoracic, and mediastinal disorders
Cough [Includes multiple similar adverse reaction terms.] | 18 | 0
Dyspnea | 13 | 0
General disorders and administration site conditions
Fatigue [Fatigue: fatigue, asthenia, and lethargy.] | 14 | 0.9
Nervous system disorders
Headache | 11 | 1.8

Clinically significant adverse reactions occurring in <10% of BRUKINSA recipients in this cohort included urinary tract infection (8%), edema (7%), atrial fibrillation or flutter (4.5%), and COVID-19 (3.6%).

Table 12 summarizes select laboratory abnormalities in this cohort.

Table 12: Select Laboratory Abnormalities (≥20%) that Worsened from Baseline in Patients with Previously Untreated CLL/SLL and 17p Deletion in SEQUOIA
Laboratory Abnormality [The denominator used to calculate the rate varied from 110 to 111 based on the number of patients with a baseline value and at least one post-treatment value. Grading is based on NCI CTCAE criteria.] | BRUKINSA
Laboratory Abnormality [The denominator used to calculate the rate varied from 110 to 111 based on the number of patients with a baseline value and at least one post-treatment value. Grading is based on NCI CTCAE criteria.] | All Grades (%) | Grade 3 or 4 (%)
Hematologic abnormalities
Neutrophils decreased | 42 | 19 [Grade 4, 9%.]
Hemoglobin decreased | 26 | 3.6
Platelets decreased | 23 | 0.9
Chemistry abnormalities
Glucose increased [Nonfasting conditions.] | 52 | 6
Magnesium increased | 31 | 0
Creatinine increased | 27 | 0.9

ALPINE

The safety of BRUKINSA monotherapy was evaluated in patients with previously treated CLL/SLL in a randomized, multicenter, open-label, actively controlled trial [see Clinical Studies (14.4)]. In ALPINE, 324 patients received BRUKINSA monotherapy, 160 mg orally twice daily and 324 patients received ibrutinib monotherapy, 420 mg orally daily until disease progression or unacceptable toxicity.

In ALPINE, the median duration of exposure was 24 months for BRUKINSA. Adverse reactions leading to death in the BRUKINSA arm occurred in 24 (7%) patients. Adverse reactions leading to death that occurred in >1% of patients were pneumonia (2.8%) and COVID-19 infection (1.9%).

One hundred and four patients in the BRUKINSA arm (32%) reported ≥1 serious adverse reaction. Serious adverse reactions occurring in ≥5% of patients were pneumonia (10%), COVID-19 (7%), and second primary malignancies (5%).

Adverse reactions led to treatment discontinuation in 13% of patients, dose reduction in 11%, and dose interruption in 42%. The leading cause of treatment discontinuation was pneumonia. The leading causes of dose modification (≥5% of all patients) were respiratory infections (COVID-19, pneumonia) and neutropenia.

Table 13 summarizes select adverse reactions in ALPINE.

Table 13: Adverse Reactions in ≥10% of Patients with Relapsed or Refractory CLL/SLL Who Received BRUKINSA in ALPINE
System Organ Class Preferred Term | BRUKINSA (N=324) |  | Ibrutinib (N=324)
System Organ Class Preferred Term | All Grades (%) | Grade 3 or 4 (%) | All Grades (%) | Grade 3 or 4 (%)
Infections and infestations
Upper respiratory tract infection [Upper respiratory tract infection: upper respiratory tract infection, sinusitis, pharyngitis, rhinitis, nasopharyngitis, laryngitis, tonsillitis, and related terms.] | 27 | 1.2 | 22 | 1.2
Pneumonia [Pneumonia: Pneumonia, COVID-19 pneumonia, lower respiratory tract infection, lung infiltration, and related terms including specific types of infection.] | 18 [Includes fatal outcomes: pneumonia (9 patients), COVID-19 (8 patients), and hemorrhage (1 patient).] | 9 | 19 [Includes fatal outcomes: pneumonia (10 patients), COVID-19 (9 patients), and hemorrhage (2 patients).] | 11
COVID-19 [COVID-19: COVID-19, COVID-19 pneumonia, postacute COVID-19 syndrome, SARS-CoV-2 test positive.] | 14 | 7 | 10 | 4.6
Musculoskeletal and connective tissue disorders
Musculoskeletal pain [Musculoskeletal pain: musculoskeletal pain, arthralgia, back pain, pain in extremity, myalgia, neck pain, spinal pain, bone pain, and musculoskeletal discomfort.] | 26 | 0.6 | 28 | 0.6
Vascular disorders
Hemorrhage [Hemorrhage: all terms containing hematoma, hemorrhage, hemorrhagic, and related terms indicative of bleeding.] | 24 | 2.5 | 26 | 3.7
Hypertension [Includes multiple similar adverse reaction terms.] | 19 | 13 | 20 | 13
Skin and subcutaneous tissue disorders
Rash [Rash: Rash, Dermatitis, and related terms.] | 20 | 1.2 | 21 | 0.9
Bruising [Bruising: all terms containing bruise, bruising, contusion, or ecchymosis.] | 16 | 0 | 14 | 0
Gastrointestinal disorders
Diarrhea | 14 | 1.5 | 22 | 0.9
General disorders
Fatigue [Fatigue: asthenia, fatigue, lethargy.] | 13 | 0.9 | 14 | 0.9
Respiratory, thoracic, and mediastinal disorders
Cough | 11 | 0.3 | 11 | 0
Nervous system disorders
Dizziness | 10 | 0 | 7 | 0

Clinically relevant adverse reactions in <10% of patients who received BRUKINSA included urinary tract infection (9%), supraventricular arrhythmias (9%) including atrial fibrillation or flutter (4.6%), abdominal pain (8%), headache (8%), pruritus (6.2%), constipation (5.9%), and edema (4.6%).

Table 14 summarizes select laboratory abnormalities in ALPINE.

Table 14: Select Laboratory Abnormalities (≥20%) that Worsened from Baseline in Patients Who Received BRUKINSA in ALPINE
Laboratory Abnormality [The denominator used to calculate the rate was 321 in the BRUKINSA arm, and varied from 320 to 321 in the ibrutinib arm, based on the number of patients with a baseline value and at least one post-treatment value. Grading is based on NCI CTCAE criteria.] | BRUKINSA |  | Ibrutinib
Laboratory Abnormality [The denominator used to calculate the rate was 321 in the BRUKINSA arm, and varied from 320 to 321 in the ibrutinib arm, based on the number of patients with a baseline value and at least one post-treatment value. Grading is based on NCI CTCAE criteria.] | All Grades (%) | Grade 3 or 4 (%) | All Grades (%) | Grade 3 or 4 (%)
Hematologic abnormalities
Neutrophils decreased | 43 | 15 | 33 | 16
Hemoglobin decreased | 28 | 4 | 32 | 3.7
Lymphocytes increased | 24 | 19 | 26 | 19
Platelets decreased | 22 | 4 | 24 | 3.4
Chemistry abnormalities
Glucose increased | 52 | 5 | 29 | 2.8
Creatinine increased | 26 | 0 | 23 | 0
Phosphate decreased | 21 | 2.5 | 13 | 2.2
Calcium decreased | 21 | 0.6 | 29 | 0

Follicular Lymphoma

The safety of BRUKINSA in combination with obinutuzumab was evaluated in 143 adult patients with relapsed or refractory follicular lymphoma (FL) in study BGB-3111-212 (ROSEWOOD), a randomized, multicenter, open-label trial [see Clinical Studies (14.5)]. The trial required an absolute neutrophil count ≥1 × 10^9/L, platelet count ≥50 × 10^9/L, and CLcr ≥30 mL/min and excluded patients requiring a strong CYP3A inhibitor or inducer.

Patients were randomized to receive either BRUKINSA 160 mg twice daily until disease progression or unacceptable toxicity plus obinutuzumab (n=143) or obinutuzumab monotherapy (n=71). Obinutuzumab was dosed at 1,000 mg intravenously on Days 1, 8, and 15 of Cycle 1; on Day 1 of Cycles 2 to 6; and then every 8 weeks for up to 20 doses. At the discretion of the investigator, obinutuzumab was administered intravenously on Day 1 (100 mg) and on Day 2 (900 mg) of Cycle 1 instead of 1,000 mg on Day 1 of Cycle 1.

In patients who received BRUKINSA in combination with obinutuzumab, the median age was 63, 49% were female, 63% were White, and 21% were Asian. Most patients (97%) had an ECOG performance status of 0 to 1. The median duration of BRUKINSA treatment was 12 months, with 24% of patients treated for at least 2 years.

Serious adverse reactions occurred in 35% of patients who received BRUKINSA in combination with obinutuzumab. Serious adverse reactions in ≥5% of patients included pneumonia (11%) and COVID-19 (10%). Fatal adverse reactions occurred in 4.2% of patients, with the leading cause of death being COVID-19 (2.1%).

Adverse reactions led to permanent discontinuation of BRUKINSA in 17% of patients, dose reduction in 9%, and dose interruption in 40%. Adverse reactions leading to permanent discontinuation in ≥2% of patients were pneumonia, COVID-19, and second primary malignancy. The leading causes of BRUKINSA dosage modification (42% of all patients) were pneumonia, COVID-19, thrombocytopenia, and neutropenia.

Table 15 summarizes adverse reactions in BGB-3111-212.

Table 15: Adverse Reactions in ≥10% of Patients with Relapsed or Refractory FL Who Received BRUKINSA in Study BGB-3111-212
System Organ Class Preferred Term | BGB-3111-212
System Organ Class Preferred Term | BRUKINSA + Obinutuzumab (N=143) |  | Obinutuzumab (N=71)
System Organ Class Preferred Term | All Grades (%) | Grade 3 or 4 (%) | All Grades (%) | Grade 3 or 4 (%)
General disorders and administration site conditions
Fatigue [Includes multiple related terms.] , [Fatigue: Fatigue, asthenia, and lethargy.] | 27 | 1.4 | 25 | 1.4
Pyrexia | 13 | 0 | 20 | 0
Musculoskeletal and connective tissue disorders
Musculoskeletal pain, [Musculoskeletal pain: Back pain, musculoskeletal pain, musculoskeletal discomfort, noncardiac chest pain, neck pain, pain in extremity, myalgia, spinal pain, bone pain, arthralgia, and related terms.] | 22 | 3.5 | 23 | 1.4
Vascular disorders
Hemorrhage, [Hemorrhage: All terms containing hematoma, hemorrhage, hemorrhagic, and related terms indicative of bleeding.] | 20 | 1.4 | 10 | 1.4
Gastrointestinal disorders
Diarrhea | 18 | 2.8 | 17 | 1.4
Constipation | 13 | 0 | 9 | 0
Abdominal pain | 11 | 2.1 | 11 | 0
Infections and infestations
Upper respiratory tract infection, [Upper respiratory tract infection: Upper respiratory tract infection, sinusitis, pharyngitis, laryngitis, rhinitis, nasopharyngitis, laryngopharyngitis, tonsillitis bacterial, and related terms.] | 17 | 2.8 | 10 | 0
Pneumonia, [Pneumonia: Pneumonia, COVID-19 pneumonia, lung infiltration, lung consolidation, and related terms including specific types of infection.] , [Includes fatal outcomes: COVID-19 (3 patients), pneumonia (2 patients), dyspnea (1 patient).] | 15 | 13 | 11 | 7
COVID-19, | 13 | 9 | 11 | 4.2
Herpes virus infection [Herpes virus infection: Herpes viral infection, herpes zoster, herpes simplex, herpes simplex reactivation, varicella, and Epstein-Barr viremia.] | 11 | 2.1 | 1.4 | 0
Urinary tract infection [Urinary tract infection: Urinary tract infection, cystitis, pyelonephritis, and related terms.] | 10 | 1.4 | 7 | 0
Respiratory, thoracic, and mediastinal disorders
Cough | 14 | 0 | 14 | 0
Dyspnea, | 11 | 2.1 | 13 | 0
Skin and subcutaneous tissue disorders
Rash, [Rash: Rash, erythema, dermatitis, drug eruption, skin reaction, and related terms.] | 11 | 0 | 14 | 0

Clinically relevant adverse reactions in <10% of patients who received BRUKINSA in combination with obinutuzumab included bruising, edema, pruritus, petechiae, vomiting, headache, arthralgia, hypertension, sepsis, cardiac arrhythmias, renal insufficiency, febrile neutropenia, transaminase elevation, and pneumonitis.

Table 16: Select Laboratory Abnormalities (≥20%) that Worsened from Baseline in Patients Who Received BRUKINSA in Study BGB-3111-212
Laboratory Abnormality [The denominator used to calculate the rate was 122 in the BRUKINSA + obinutuzumab arm, and varied from 56 to 58 in the obinutuzumab arm, based on the number of patients with a baseline value and at least one post-treatment value. Grading is based on NCI CTCAE criteria.] | BGB-3111-212
Laboratory Abnormality [The denominator used to calculate the rate was 122 in the BRUKINSA + obinutuzumab arm, and varied from 56 to 58 in the obinutuzumab arm, based on the number of patients with a baseline value and at least one post-treatment value. Grading is based on NCI CTCAE criteria.] | BRUKINSA + Obinutuzumab |  | Obinutuzumab
Laboratory Abnormality [The denominator used to calculate the rate was 122 in the BRUKINSA + obinutuzumab arm, and varied from 56 to 58 in the obinutuzumab arm, based on the number of patients with a baseline value and at least one post-treatment value. Grading is based on NCI CTCAE criteria.] | All Grades (%) | Grade 3 or 4 (%) | All Grades (%) | Grade 3 or 4 (%)
Hematologic abnormalities
Platelets decreased | 65 | 11 | 43 | 11
Neutrophils decreased | 47 | 17 | 42 | 14
Hemoglobin decreased | 31 | 0.8 | 23 | 0
Lymphocytes decreased | 30 | 11 | 51 | 25
Chemistry
Glucose increased [Nonfasting conditions.] | 53 | 8 | 41 | 9
Alanine aminotransferase increased | 23 | 0 | 28 | 0
Phosphate decreased | 21 | 0.8 | 14 | 0

6.2 Postmarketing Experience

The following adverse reactions have been identified during postapproval use of BRUKINSA. Because these reactions are reported voluntarily from a population of uncertain size, it is not always possible to reliably estimate their frequency or establish a causal relationship to drug exposure.

- Hepatobiliary disorder: drug-induced liver injury

7 DRUG INTERACTIONS

7.1 Effect of Other Drugs on BRUKINSA

Table 17: Drug Interactions that Affect Zanubrutinib
Moderate and Strong CYP3A Inhibitors
Clinical Impact | - Coadministration with a moderate or strong CYP3A inhibitor increases zanubrutinib Cmax and AUC [see Clinical Pharmacology (12.3)] which may increase the risk of BRUKINSA toxicities.
Prevention or management | - Reduce BRUKINSA dosage when coadministered with moderate or strong CYP3A inhibitors [see Dosage and Administration (2.3)].
Moderate and Strong CYP3A Inducers
Clinical Impact | - Coadministration with a moderate or strong CYP3A inducer decreases zanubrutinib Cmax and AUC [see Clinical Pharmacology (12.3)] which may reduce BRUKINSA efficacy.
Prevention or management | - Avoid coadministration of BRUKINSA with strong CYP3A inducers [see Dosage and Administration (2.3)]. - Avoid coadministration of BRUKINSA with moderate CYP3A inducers [see Dosage and Administration (2.3)]. If these inducers cannot be avoided, increase BRUKINSA dosage to 320 mg twice daily [see Dosage and Administration (2.3)].

8 USE IN SPECIFIC POPULATIONS

8.1 Pregnancy

Risk Summary

Based on findings in animals, BRUKINSA can cause fetal harm when administered to pregnant women. There are no available data on BRUKINSA use in pregnant women to evaluate for a drug-associated risk of major birth defects, miscarriage, or adverse maternal or fetal outcomes. In animal reproduction studies, oral administration of zanubrutinib to pregnant rats during the period of organogenesis was associated with fetal heart malformation at approximately 5-fold human exposures (see Data). Women should be advised to avoid pregnancy while taking BRUKINSA. If BRUKINSA is used during pregnancy, or if the patient becomes pregnant while taking BRUKINSA, the patient should be apprised of the potential hazard to the fetus.

The estimated background risk of major birth defects and miscarriage for the indicated population is unknown. All pregnancies have a background risk of birth defect, loss, or other adverse outcomes. In the U.S. general population, the estimated background risk of major birth defects and miscarriage in clinically recognized pregnancies is 2% to 4% and 15% to 20%, respectively.

Data

Animal Data

Embryo-fetal development toxicity studies were conducted in both rats and rabbits. Zanubrutinib was administered orally to pregnant rats during the period of organogenesis at doses of 30, 75, and 150 mg/kg/day. Malformations in the heart (2 or 3-chambered hearts) were noted at all dose levels in the absence of maternal toxicity. The dose of 30 mg/kg/day is approximately 5 times the exposure (AUC) in patients receiving the recommended dose of 160 mg twice daily.

Administration of zanubrutinib to pregnant rabbits during the period of organogenesis at 30, 70, and 150 mg/kg/day resulted in postimplantation loss at the highest dose. The dose of 150 mg/kg is approximately 32 times the exposure (AUC) in patients at the recommended dose and was associated with maternal toxicity.

In a pre and postnatal developmental toxicity study, zanubrutinib was administered orally to rats at doses of 30, 75, and 150 mg/kg/day from implantation through weaning. The offspring from the middle and high dose groups had decreased body weights preweaning, and all dose groups had adverse ocular findings (e.g., cataract, protruding eye). The dose of 30 mg/kg/day is approximately 5 times the AUC in patients receiving the recommended dose.

8.2 Lactation

Risk Summary

There are no data on the presence of zanubrutinib or its metabolites in human milk, the effects on the breastfed child, or the effects on milk production. Because of the potential for serious adverse reactions from BRUKINSA in a breastfed child, advise lactating women not to breastfeed during treatment with BRUKINSA and for two weeks following the last dose.

8.3 Females and Males of Reproductive Potential

BRUKINSA can cause embryo-fetal harm when administered to pregnant women [see Use in Specific Populations (8.1)].

Pregnancy Testing

Pregnancy testing is recommended for females of reproductive potential prior to initiating BRUKINSA therapy.

Contraception

Females

Advise female patients of reproductive potential to use effective contraception during treatment with BRUKINSA and for 1 week following the last dose of BRUKINSA. If this drug is used during pregnancy, or if the patient becomes pregnant while taking this drug, the patient should be informed of the potential hazard to a fetus.

Males

Advise men to avoid fathering a child while receiving BRUKINSA and for 1 week following the last dose of BRUKINSA.

8.4 Pediatric Use

Safety and effectiveness of BRUKINSA in pediatric patients have not been established.

8.5 Geriatric Use

Of the 1729 patients with MCL, MZL, WM, CLL/SLL, and FL in clinical studies with BRUKINSA, 59% were ≥65 years of age, and 21% were ≥75 years of age. Patients ≥65 years of age had numerically higher rates of Grade 3 or higher adverse reactions and serious adverse reactions (57% and 38%, respectively) than patients <65 years of age (51% and 29%, respectively). No overall differences in effectiveness were observed between younger and older patients.

8.6 Renal Impairment

No dosage modification is recommended in patients with mild, moderate, or severe renal impairment (CLcr ≥15 mL/min, estimated by Cockcroft-Gault). Monitor for BRUKINSA adverse reactions in patients on dialysis [see Clinical Pharmacology (12.3)].

8.7 Hepatic Impairment

Dosage modification of BRUKINSA is recommended in patients with severe hepatic impairment [see Dosage and Administration (2.2)]. The safety of BRUKINSA has not been evaluated in patients with severe hepatic impairment. No dosage modification is recommended in patients with mild to moderate hepatic impairment. Monitor for BRUKINSA adverse reactions in patients with hepatic impairment [see Clinical Pharmacology (12.3)].

11 DESCRIPTION

BRUKINSA (zanubrutinib) is a kinase inhibitor. The empirical formula of zanubrutinib is C27H29N5O3 and the chemical name is (S)-7-(1-acryloylpiperidin-4-yl)-2-(4-phenoxyphenyl)-4,5,6,7-tetrahydropyrazolo[1,5-a]pyrimidine-3-carboxamide. Zanubrutinib is a white to off-white powder, with a pH of 7.8 in saturated solution. The aqueous solubility of zanubrutinib is pH dependent, from very slightly soluble to practically insoluble.

The molecular weight of zanubrutinib is 471.55 Daltons.

Zanubrutinib has the following structure:

Each BRUKINSA capsule for oral administration contains 80 mg zanubrutinib and the following inactive ingredients: colloidal silicon dioxide, croscarmellose sodium, magnesium stearate, microcrystalline cellulose, and sodium lauryl sulfate. The capsule shell contains edible black ink, gelatin, and titanium dioxide.

Each BRUKINSA tablet for oral administration contains 160 mg zanubrutinib and the following inactive ingredients: colloidal silicon dioxide, croscarmellose sodium, lactose monohydrate, magnesium stearate, microcrystalline cellulose, povidone, and sodium lauryl sulfate. The film coating contains FD&C Blue No. 1, FD&C Blue No. 2, hypromellose, titanium dioxide, and triacetin.

12 CLINICAL PHARMACOLOGY

12.1 Mechanism of Action

Zanubrutinib is a small-molecule inhibitor of Bruton's tyrosine kinase (BTK). Zanubrutinib forms a covalent bond with a cysteine residue in the BTK active site, leading to inhibition of BTK activity. BTK is a signaling molecule of the B-cell antigen receptor (BCR) and cytokine receptor pathways. In B-cells, BTK signaling results in activation of pathways necessary for B-cell proliferation, trafficking, chemotaxis, and adhesion. In nonclinical studies, zanubrutinib inhibited malignant B-cell proliferation and reduced tumor growth.

12.2 Pharmacodynamics

BTK Occupancy in PBMCs and Lymph Nodes

The median steady-state BTK occupancy in peripheral blood mononuclear cells was maintained at 100% over 24 hours at a total daily dose of 320 mg in patients with B-cell malignancies. The median steady-state BTK occupancy in lymph nodes was 94% to 100% following the approved recommended dosage.

Cardiac Electrophysiology

At the approved recommended doses (160 mg twice daily or 320 mg once daily), there were no clinically relevant effects on the QTc interval. The effect of BRUKINSA on the QTc interval above the therapeutic exposure has not been evaluated.

In Vitro Platelet Aggregation

In blood samples from healthy donors, patients on anticoagulant or antiplatelet therapy, and those with severe renal dysfunction, zanubrutinib demonstrated inhibition of platelet aggregation mediated by collagen, CRP-XL, or rhodocytin. Zanubrutinib did not show meaningful inhibition of platelet aggregation for ADP and PAR4-AP.

12.3 Pharmacokinetics

Zanubrutinib maximum plasma concentration (Cmax) and area under the plasma drug concentration over time curve (AUC) increase proportionally over a dosage range from 40 mg to 320 mg (0.13 to 1 time the recommended total daily dose). Limited systemic accumulation of zanubrutinib was observed following repeated administration.

The geometric mean (%CV) zanubrutinib steady-state daily AUC is 2,099 (42%) ng∙h/mL following 160 mg twice daily and 1,917 (59%) ng∙h/mL following 320 mg once daily. The geometric mean (%CV) zanubrutinib steady-state Cmax is 295 (55%) ng/mL following 160 mg twice daily and 537 (55%) ng/mL following 320 mg once daily.

Absorption

The median tmax of zanubrutinib is 2 hours.

Effect of Food

BRUKINSA Capsules:

Zanubrutinib AUC decreased 7% and Cmax increased 3% following administration of BRUKINSA capsules with a high-fat meal (1,000 calories, 50% fat) in healthy subjects.

BRUKINSA Tablets:

Zanubrutinib AUC increased up to 17% and Cmax up to 79% following administration of BRUKINSA tablets with a high-fat meal (1,000 calories, 50% fat) in healthy subjects.

Distribution

The geometric mean (%CV) apparent volume of distribution (Vz/F) of zanubrutinib is 537 (73%) L. The plasma protein binding of zanubrutinib is approximately 94% and the blood-to-plasma ratio is 0.7 to 0.8.

Elimination

The mean half-life (t½) of zanubrutinib is approximately 2 to 4 hours following a single oral zanubrutinib dose of 160 mg or 320 mg. The geometric mean (%CV) apparent oral clearance (CL/F) of zanubrutinib is 128 (58%) L/h.

Metabolism

Zanubrutinib is primarily metabolized by cytochrome P450(CYP)3A.

Excretion

Following a single radiolabeled zanubrutinib dose of 320 mg to healthy subjects, approximately 87% of the dose was recovered in feces (38% unchanged) and 8% in urine (less than 1% unchanged).

Specific Populations

No clinically significant differences in the pharmacokinetics of zanubrutinib were observed based on age (19 to 90 years), sex, race (Asian, White, and Other), body weight (36 to 144 kg), or mild, moderate or severe renal impairment (CLcr ≥15 mL/min as estimated by Cockcroft-Gault). The effect of dialysis on zanubrutinib pharmacokinetics is unknown.

Hepatic Impairment

The total AUC of zanubrutinib increased by 11% in subjects with mild hepatic impairment (Child-Pugh class A), by 21% in subjects with moderate hepatic impairment (Child-Pugh class B), and by 60% in subjects with severe hepatic impairment (Child-Pugh class C) relative to subjects with normal liver function. The unbound AUC of zanubrutinib increased by 23% in subjects with mild hepatic impairment (Child-Pugh class A), by 43% in subjects with moderate hepatic impairment (Child-Pugh class B) and by 194% in subjects with severe hepatic impairment (Child-Pugh class C) relative to subjects with normal liver function.

Drug Interaction Studies

Clinical Studies and Model-Informed Approaches

CYP3A Inhibitors: Coadministration of multiple doses of CYP3A inhibitors increases zanubrutinib Cmax and AUC (Table 18).

Table 18: Observed or Predicted Increase in Zanubrutinib Exposure After Coadministration of CYP3A Inhibitors
Coadministered CYP3A Inhibitor | Increase in Zanubrutinib Cmax | Increase in Zanubrutinib AUC
 | Observed
Itraconazole (200 mg once daily) [The assessment was conducted in healthy subjects with a single dose of zanubrutinib 20 mg.] | 157% | 278%
Fluconazole (400 mg once daily) [The assessment was conducted in patients with B-cell lymphoma administered multiple doses of zanubrutinib at the respective recommended zanubrutinib dosages in Table 1.] | 81% | 88%
Diltiazem (180 mg once daily) | 62% | 62%
Voriconazole (200 mg twice daily) | 229% | 230%
Clarithromycin (250 mg twice daily) | 101% | 92%
 | Predicted
Posaconazole suspension (100 mg once daily) [The predicted values were based on simulations with patients administered multiple doses of zanubrutinib at the respective recommended dosages in Table 1.] | 169% | 180%
Posaconazole suspension (100 mg twice daily) | 207% | 279%
Posaconazole delayed-release tablets (300 mg once daily) | 232% | 407%
Posaconazole intravenously (300 mg once daily) | 205% | 333%
Itraconazole (200 mg once daily) | 273% | 320%

CYP3A Inducers: Coadministration of multiple doses of rifampin (strong CYP3A inducer) decreased the zanubrutinib Cmax by 92% and AUC by 93%. Coadministration of multiple doses of rifabutin (moderate CYP3A inducer) decreased the zanubrutinib Cmax by 48% and AUC by 44%.

Coadministration of multiple doses of efavirenz (moderate CYP3A inducer) is predicted to decrease zanubrutinib Cmax by 58% and AUC by 60%.

CYP3A Substrates: Coadministration of multiple doses of zanubrutinib decreased midazolam (CYP3A substrate) Cmax by 30% and AUC by 47%.

CYP2C19 Substrates: Coadministration of multiple doses of zanubrutinib decreased omeprazole (CYP2C19 substrate) Cmax by 20% and AUC by 36%.

Other CYP Substrates: No clinically significant differences were observed with warfarin (CYP2C9 substrate) pharmacokinetics when coadministered with zanubrutinib.

Transporter Systems: Coadministration of multiple doses of zanubrutinib increased digoxin (P-gp substrate) Cmax by 34% and AUC by 11%. No clinically significant differences in the pharmacokinetics of rosuvastatin (BCRP substrate) were observed when coadministered with zanubrutinib.

Gastric Acid Reducing Agents: No clinically significant differences in zanubrutinib pharmacokinetics were observed when coadministered with gastric acid reducing agents (proton pump inhibitors, H2-receptor antagonists).

In Vitro Studies

CYP Enzymes: Zanubrutinib is an inducer of CYP2B6 and CYP2C8.

Transporter Systems: Zanubrutinib is likely to be a substrate of P-gp. Zanubrutinib is not a substrate or inhibitor of OAT1, OAT3, OCT2, OATP1B1, or OATP1B3.

13 NONCLINICAL TOXICOLOGY

13.1 Carcinogenesis, Mutagenesis, Impairment of Fertility

Carcinogenicity studies have not been conducted with zanubrutinib.

Zanubrutinib was not mutagenic in a bacterial mutagenicity (Ames) assay, was not clastogenic in a chromosome aberration assay in mammalian (CHO) cells, nor was it clastogenic in an in vivo bone marrow micronucleus assay in rats.

A combined male and female fertility and early embryonic development study was conducted in rats at oral zanubrutinib doses of 30 to 300 mg/kg/day. Male rats were dosed 4 weeks prior to mating and through mating and female rats were dosed 2 weeks prior to mating and to gestation day 7. No effect on male or female fertility was noted at lower doses, but at the highest dose tested, morphological abnormalities in sperm and increased postimplantation loss were noted. The high dose of 300 mg/kg/day is approximately 10 times the human recommended dose, based on body surface area.

14 CLINICAL STUDIES

14.1 Mantle Cell Lymphoma

The efficacy of BRUKINSA was assessed in BGB-3111-206 [NCT03206970], a Phase 2, open-label, multicenter, single-arm trial of 86 previously treated patients with MCL who had received at least one prior therapy. BRUKINSA was given orally at a dose of 160 mg twice daily until disease progression or unacceptable toxicity.

The median age of patients was 60.5 years (range: 34 to 75) and the majority were male (78%). The median time since diagnosis to study entry was 30 months (range: 3 to 102) and the median number of prior therapies was 2 (range: 1 to 4). The most common prior regimens were CHOP-based (91%) followed by rituximab-based (74%). The majority of patients had extranodal involvement (71%) and refractory disease (52%). Blastoid variant of MCL was present in 14% of patients. The MIPI score was low in 58%, intermediate in 29%, and high risk in 13%.

The efficacy of BRUKINSA was also assessed in BGB-3111-AU-003 [NCT02343120], a Phase 1/2, open-label, dose-escalation, global, multicenter, single-arm trial of B cell malignancies including 32 previously treated MCL patients treated with BRUKINSA. BRUKINSA was given orally at doses of 160 mg twice daily or 320 mg daily. The median age of patients with previously treated MCL was 70 years (range: 42 to 86) and 38% of patients were ≥75 years old. Most patients were male (69%) and White (78%). The MIPI score was low in 28%, intermediate in 41%, and high risk in 31%.

Tumor response was according to the 2014 Lugano Classification for both studies, and the primary efficacy endpoint was overall response rate as assessed by an Independent Review Committee (IRC).

Table 19: Efficacy Results per IRC in Patients with MCL
 | Study BGB-3111-206 (N=86) | Study BGB-3111-AU-003 (N=32)
ORR (95% CI) | 84% (74, 91) | 84% (67, 95)
CR | 59% | 22% [FDG-PET scans were not required for response assessment.]
PR | 24% | 62%
Median DOR in months (95% CI) | 19.5 (16.6, NE) | 18.5 (12.6, NE)
ORR: overall response rate, CR: complete response, PR: partial response, DOR: duration of response, CI: confidence interval, NE: not estimable.

14.2 Waldenström's Macroglobulinemia

The efficacy of BRUKINSA was evaluated in ASPEN [NCT03053440], a randomized, active control, open-label trial, comparing BRUKINSA and ibrutinib in patients with MYD88 L265P mutation (MYD88MUT) WM. Patients in Cohort 1 (n=201) were randomized 1:1 to receive BRUKINSA 160 mg twice daily or ibrutinib 420 mg once daily until disease progression or unacceptable toxicity. Randomization was stratified by number of prior therapies (0 vs 1-3 vs >3) and CXCR4 status (presence or absence of a WHIM-like mutation as measured by Sanger assay).

The major efficacy outcome was the response rate defined as PR or better as assessed by IRC based on standard consensus response criteria from the International Workshop on Waldenström's Macroglobulinemia (IWWM)-6 criteria. An additional efficacy outcome measure was duration of response (DOR).

The median age was 70 years (range: 38 to 90) and 68% were male. Of those enrolled, 2% were Asian, 91% were White, and 7% were of unknown race. ECOG performance status of 0 or 1 was present in 93% patients at baseline and 7% had a baseline ECOG performance status of 2. A total of 82% had relapsed/refractory disease with 85% having received prior alkylating agents and 91% prior anti-CD20 therapy. The median number of prior therapies in those with relapsed/refractory disease was 1 (range: 1 to 8). A total of 91 (45%) patients had International Prognostic Scoring System (IPSS) high WM.

The study did not meet statistical significance for the prespecified efficacy outcome of superior CR+VGPR as assessed by IRC, tested first in patients with R/R disease in ASPEN.

Table 20 shows the response rates in ASPEN based on IRC assessment.

Table 20: Response Rate and Duration of Response Based on IRC Assessment in ASPEN
 | Standard IWWM-6 [IWWM-6 criteria (Owen et al, 2013) require complete resolution of extramedullary disease (EMD) if present at baseline for VGPR to be assessed.] |  | Modified IWWM-6 [Modified IWWM-6 criteria (Treon, 2015) require a reduction in EMD if present at baseline for VGPR to be assessed.]
Response Category | BRUKINSA (N=102) | Ibrutinib (N=99) | BRUKINSA (N=102) | Ibrutinib (N=99)
Response rate (CR+VGPR+PR), n (%) | 79 (77.5) | 77 (77.8) | 79 (77.5) | 77 (77.8)
95% CI (%) [2-sided Clopper-Pearson 95% confidence interval.] | (68.1, 85.1) | (68.3, 85.5) | (68.1, 85.1) | (68.3, 85.5)
Complete Response (CR) | 0 (0) | 0 (0) | 0 (0) | 0 (0)
Very Good Partial Response (VGPR) | 16 (15.7) | 7 (7.1) | 29 (28.4) | 19 (19.2)
Partial Response (PR) | 63 (61.8) | 70 (70.7) | 50 (49) | 58 (58.6)
Duration of response (DOR), Event-free at 12 months (95% CI) [Estimated by Kaplan-Meier method with 95% CIs estimated using the method of Brookmeyer and Crowley.] | 94.4% (85.8, 97.9) | 87.9% (77, 93.8) | 94.4% (85.8, 97.9) | 87.9% (77, 93.8)

ASPEN Cohort 2

Cohort 2 enrolled patients with MYD88 wildtype (MYD88WT) or MYD88 mutation unknown WM (N=26 and 2, respectively) and received BRUKINSA 160 mg twice daily. The median age was 72 years (range: 39 to 87) with 43% >75 years, 50% were male, 96% were White, and 4% were not reported (unknown race). Eighty-six percent of patients had a baseline ECOG performance status 0 or 1 and 14% had a baseline performance status of 2. Twenty-three of the 28 patients in Cohort 2 had relapsed or refractory disease.

In Cohort 2, response (CR+VGPR+PR) as assessed by IRC using IWWM-6 or modified IWWM-6 was seen in 50% (13 out of 26 response evaluable patients; 95% CI: 29.9, 70.1).

14.3 Marginal Zone Lymphoma

The efficacy of BRUKINSA was assessed in Study BGB-3111-214 [NCT03846427], an open-label, multicenter, single-arm trial that evaluated 66 patients with MZL who received at least one prior anti–CD20-based therapy. BRUKINSA was given orally at a dosage of 160 mg twice daily until disease progression or unacceptable toxicity. The median age was 70 years (range: 37 to 85); 55% were male; 38% had extranodal MZL, 38% nodal, 18% splenic, and 6% had unknown subtype. The median number of prior systemic therapies was 2 (range: 1 to 6), with 27% having 3 or more lines of systemic therapy; 88% had prior rituximab-based chemotherapy; 32% had refractory disease at study entry.

The efficacy of BRUKINSA was also assessed in BGB-3111-AU-003 [NCT02343120], an open-label, multicenter, single-arm trial that included 20 patients with previously treated MZL (45% having extranodal MZL, 25% nodal, 30% splenic). BRUKINSA was given orally at dosages of 160 mg twice daily or 320 mg once daily. The median age was 70 years (range: 52 to 85); 50% were male. The median number of prior systemic therapies was 2 (range: 1 to 5), with 20% having 3 or more lines of systemic therapy; 95% had prior rituximab-based chemotherapy.

Efficacy was based on overall response rate (ORR) and duration of response as assessed by an Independent Review Committee (IRC) using 2014 Lugano criteria (Table 21).

Table 21: Efficacy Results per IRC in Patients with MZL
Parameter | Study BGB-3111-214 (N=66) | Study BGB-3111-AU-003 (N=20)
Overall response rate (CT-based) [Per 2014 CT-based Lugano criteria. FDG-PET scans were not considered for this response assessment.]
ORR, n | 37 (56%) | 16 (80%)
(95% CI, %) | (43, 68) | (56, 94)
CR, n | 13 (20%) | 4 (20%)
PR, n | 24 (36%) | 12 (60%)
Time to response
Median (range), months | 2.9 (1.8, 11.1) | 2.9 (2.6, 23.1)
Duration of response [Based on Kaplan-Meier estimation. Estimated median follow-up for DOR was 8.3 months for Study BGB-3111-214 and 31.4 months for Study BGB-3111-AU-003.]
Median DOR (95% CI), months | NE (NE, NE) | NE (8.4, NE)
Rate at 12 months (95% CI) | 85% (67, 93) | 72% (40, 88)
ORR: overall response rate, CR: complete response, PR: partial response, DOR: duration of response, CI: confidence interval, NE: not estimable.

In study BGB-3111-214, ORR prioritizing PET-CT when available (55 patients, with the remainder assessed by CT scan) was 67% (95% CI: 54, 78) with a CR rate of 26%.

14.4 Chronic Lymphocytic Leukemia or Small Lymphocytic Lymphoma

The efficacy of BRUKINSA in patients with CLL/SLL was evaluated in two randomized controlled trials.

SEQUOIA

The efficacy of BRUKINSA in patients with previously untreated CLL/SLL was evaluated in a multicenter, open-label trial (SEQUOIA; NCT03336333). The trial required patients to be unsuitable for FCR therapy defined as either age ≥65 years or age 18 to <65 with a total Cumulative Illness Rating Scale (CIRS) >6, creatinine clearance 30 to 69 mL/min, or history of serious or recurrent infection. Patients without 17p deletion (17p del) were randomized to receive either BRUKINSA 160 mg twice daily until disease progression or unacceptable toxicity (n=241) or bendamustine plus rituximab (BR) for 6 cycles (n=238). Bendamustine was dosed at 90 mg/m^2/day intravenously on the first 2 days of each cycle, and rituximab was dosed at 375 mg/m^2 on day 1 of Cycle 1 and 500 mg/m^2 on day 1 of Cycles 2 to 6 with a 28-day cycle length. Randomization was stratified by age, Binet stage, immunoglobulin variable region heavy chain (IGHV) mutational status, and geographic region.

Additionally, the same BRUKINSA regimen was evaluated in 110 patients with previously untreated 17p del CLL/SLL in a non-randomized cohort.

Efficacy is summarized according to cohort.

Randomized Cohort: Previously Untreated CLL/SLL without 17p Deletion

In the randomized cohort of patients with previously untreated CLL/SLL without 17p deletion, the median age was 70 years; 62% were male, 89% were White, 3% were Asian, and 1% were Black. Fifty-three percent of patients had an unmutated IGHV gene and 29% had Binet Stage C disease. Baseline characteristics were generally similar between treatment arms.

Efficacy in this cohort was based on progression-free survival as assessed by an IRC. Efficacy results are presented in Table 22 and Figure 1.

Table 22: Efficacy Results per IRC in Patients with Previously Untreated CLL/SLL without 17p Deletion in SEQUOIA (Randomized Cohort)
Parameter [Efficacy was assessed using the 2008 International Workshop for Chronic Lymphocytic Leukemia (iwCLL) guidelines and 2014 Lugano criteria for SLL.] | CLL/SLL without del(17p)
Parameter [Efficacy was assessed using the 2008 International Workshop for Chronic Lymphocytic Leukemia (iwCLL) guidelines and 2014 Lugano criteria for SLL.] | BRUKINSA (N=241) | Bendamustine + Rituximab (N=238)
Progression-free survival
Number of Events, n | 36 (15%) | 71 (30%)
Disease Progression | 27 (11%) | 59 (25%)
Death | 9 (3.7%) | 12 (5%)
Median PFS (95% CI), months [Based on Kaplan-Meier estimation. Estimated median follow-up for PFS was 25 months.] | NE (NE, NE) | 33.7 (28.1, NE)
HR (95% CI) [Based on a stratified Cox-regression model with bendamustine + rituximab as the reference group.] | 0.42 (0.28, 0.63)
P-value [Based on a stratified log-rank test, with a 2-sided significance level of 0.0372.] | <0.0001
Overall response rate [Defined as CR, CRi, PR, and nPR. No patients had CRi as best response.]
ORR, n (%) | 225 (93) | 203 (85)
95% CI, % | (89, 96) | (80, 90)
CR, n (%) | 16 (7) | 36 (15)
nPR, n (%) | 3 (1.2) | 14 (6)
PR, n (%) | 206 (85) | 153 (64)
CI=Confidence interval, CR=complete response, CRi=complete response with incomplete hematopoietic recovery, HR=hazard ratio, NE=not estimable, nPR=nodular partial response, ORR=overall response rate, PFS=progression-free survival, PR=partial response.

Figure 1: Kaplan-Meier Plot of IRC-Assessed Progression-Free Survival in Patients with Previously Untreated CLL/SLL without 17p Deletion in SEQUOIA

At the time of analysis, overall survival data were immature. With an estimated median follow-up of 25.7 months, median overall survival was not reached in either arm, with fewer than 7% of patients experiencing an event.

Single-Arm Cohort: Previously Untreated CLL/SLL with 17p Deletion

In this cohort, 110 patients with previously untreated CLL/SLL and centrally confirmed 17p deletion received BRUKINSA 160 mg twice daily until disease progression or unacceptable toxicity.

The median age was 70, 71% were male, 95% were White, and 1% were Asian. Sixty percent of patients had an unmutated IGHV gene and 35% had Binet Stage C disease.

Efficacy was based on overall response rate and duration of response as assessed by an IRC. Efficacy results are presented in Table 23.

Table 23: Efficacy Results per IRC in Patients with Previously Untreated CLL/SLL and 17p Deletion in SEQUOIA
Parameter [Efficacy was assessed using the 2008 iwCLL guidelines and Lugano criteria for SLL.] | del(17p) CLL/SLL N=110
Overall response rate [Defined as CR, CRi, PR, and nPR. No patients had CRi as best response.]
ORR, n (%) | 97 (88)
(95% CI, %) | (81, 94)
CR, n (%) | 7 (6)
nPR, n (%) | 2 (1.8)
PR, n (%) | 88 (80)
Time to response
Median (range), months | 2.9 (1.9 to 13.9)
Duration of response
Median DOR (95% CI), [Kaplan-Meier estimate. Estimated median follow-up for DOR was 25.1 months.] months | NE (NE, NE)
Range, months | (5.6 to 35.9+)
Rate at 12 months, % (95% CI) | 96 (89, 98)
Rate at 18 months, % (95% CI) | 95 (88, 98)
DOR=duration of response. A + sign indicates a censored observation.

ALPINE

The efficacy of BRUKINSA in patients with relapsed or refractory CLL/SLL was evaluated in ALPINE, a randomized, multicenter, open-label, actively controlled trial (NCT03734016). The trial enrolled 652 patients with relapsed or refractory CLL/SLL after at least 1 systemic therapy. The patients were randomized in a 1:1 ratio to receive either BRUKINSA 160 mg orally twice daily (n=327) or ibrutinib 420 mg orally once daily (n=325), each administered until disease progression or unacceptable toxicity.

Randomization was stratified by age, geographic region, refractoriness to last therapy, and 17p deletion/TP53 mutation status.

Baseline characteristics were similar between treatment arms. Overall, the median age was 67 years, 68% were male, 81% were White, 14% were Asian, and 1% were Black. Forty-three percent had advanced stage disease, 73% had an unmutated IGHV gene, and 23% had 17p deletion or TP53 mutation. Patients had a median of one prior line of therapy (range: 1-8), 18% of patients had ≥3 prior lines of therapy, 78% had prior chemoimmunotherapy, and 2.3% had prior BCL2 inhibitor.

Efficacy was based on overall response rate and duration of response as determined by an IRC. For progression-free survival per IRC, the final analysis occurred with a median follow-up of 31 months. Efficacy results are shown in Table 24 and Figure 2.

Table 24: Efficacy Results per IRC in Patients with Relapsed or Refractory CLL/SLL in ALPINE
Parameter [Efficacy was based on 2008 iwCLL guidelines for CLL and the Lugano criteria for SLL.] | BRUKINSA (N=327) | Ibrutinib (N=325)
Overall response rate [Defined as CR + CRi + nPR + PR. No patients had CRi as best response.]
ORR, n (%) | 263 (80) | 237 (73)
(95% CI, %) | (76, 85) | (68, 78)
CR, n (%) | 13 (4) | 8 (2.5)
nPR, n (%) | 1 (0.3) | 0 (0)
PR, n (%) | 249 (76) | 229 (70)
Response Rate Ratio (95% CI) [Estimate stratified by randomization stratification factors.] | 1.10 (1.01, 1.20)
2-sided p-value [2-sided significance level of 0.0469 was allocated for ORR superiority testing.] | 0.0264
Duration of response
Median DOR (95% CI) [Based on Kaplan-Meier estimate. Estimated median follow-up for DOR was 14.1 months.] | NE (NE, NE) | NE (NE, NE)
Range, months | (1.4 to 30.4+) | (1.9+ to 30.8+)
Rate at 12 months, % (95% CI) | 92 (87, 95) | 86 (80, 91)
Progression-free survival
Events, n (%) | 88 (27) | 120 (37)
Median PFS (95% CI), months [Based on Kaplan-Meier estimation. Estimated median follow-up for PFS was 30.7 months.] | NE (34.3, NE) | 35 (33.2, 44.3)
HR (95% CI) [Based on a stratified Cox-regression model with ibrutinib as the reference group.] | 0.65 (0.49, 0.86)
2-sided p-value [Based on a stratified log-rank test.] | 0.0024
CI=Confidence interval, CR=complete response, CRi=complete response with incomplete hematopoietic recovery, DOR=duration of response, HR=hazard ratio, NE=not estimable, nPR=nodular partial response, ORR=overall response rate, PR=partial response. A + sign indicates a censored observation.

The median time to response was 5.5 months for BRUKINSA and 5.6 months for ibrutinib.

Figure 2: Kaplan-Meier Plot of Progression-Free Survival by IRC in ALPINE

At the time of final analysis, the median overall survival was not reached in either arm. There were a total of 108 deaths: 48 (14.7%) in the zanubrutinib arm and 60 (18.5%) in the ibrutinib arm.

14.5 Follicular Lymphoma

The efficacy of BRUKINSA, in combination with obinutuzumab, was evaluated in Study BGB-3111-212 (ROSEWOOD; NCT03332017), an open-label, multicenter, randomized trial that enrolled 217 adult patients with relapsed or refractory FL after at least 2 prior systemic treatments. The study required prior receipt of an anti-CD20 antibody and an alkylator-based combination therapy, and excluded patients with FL Grade 3b, transformed lymphoma, and prior exposure to a BTK inhibitor.

Patients were randomized in a 2:1 ratio to receive either BRUKINSA 160 mg orally twice daily until disease progression or unacceptable toxicity plus obinutuzumab, or obinutuzumab alone. Obinutuzumab was administered 1,000 mg intravenously on days 1, 8, and 15 of Cycle 1, 1,000 mg on Day 1 of Cycles 2 to 6; and then 1,000 mg every 8 weeks for up to 20 doses. At the discretion of the investigator, obinutuzumab could be administered as 100 mg on Day 1 and 900 mg on Day 2 of Cycle 1.

Randomization was stratified by the number of prior lines of therapy (2 to 3 vs ˃3), rituximab-refractory status (yes vs no), and geographic region.

Of the 217 patients randomized (145 to BRUKINSA plus obinutuzumab, 72 to obinutuzumab monotherapy), the median age was 64 years (range: 31 to 88), 50% were male, 64% were White, and 22% were Asian. In total, 83% had stage 3 or 4 disease and 57% met Groupe d'Etude des Lymphomes Folliculaires (GELF) criteria at enrollment. Patients had a median of 3 prior lines of therapy (range: 2-11), with 27% of patients having more than 3 prior lines of therapy.

In the BRUKINSA in combination with obinutuzumab arm, 5% had received lenalidomide plus rituximab, 21% had received stem cell transplantation, 53% had refractory disease to rituximab, and 37% had progression of disease within 24 months of the first systemic therapy.

Efficacy was based on overall response rate and duration of response, as determined by an IRC. Efficacy results are shown in Table 25. The median time to response in the BRUKINSA combination arm was 2.8 months (range 2 to 23 months).

Table 25: Efficacy Results per IRC in Patients with Relapsed or Refractory Follicular Lymphoma
Parameter | BRUKINSA + Obinutuzumab (N=145) | Obinutuzumab (N=72)
Overall response rate
ORR, n (%) | 100 (69) | 33 (46)
(95% CI) [Estimated using the Clopper-Pearson method.] | (61, 76) | (34, 58)
CR | 57 (39) | 14 (19)
PR | 43 (30) | 19 (26)
Risk difference, % (95% CI) [Estimated by stratified Cochran-Mantel-Haenszel method.] | 22.7 (9, 36.5)
2-sided p-value, [Significance level, 0.05.] | 0.0012
Duration of response
Median DOR (95% CI), [Estimated by Kaplan-Meier method. Estimated median follow-up for DOR was 19 months overall.] months | NE (25.3, NE) | 14 (9.2, 25.1)
CI=Confidence interval, CR=complete response, DOR=duration of response, NE=not estimable, ORR=overall response rate, PR=partial response.

The estimated DOR rate at 18 months was 69% (95% CI: 58, 78) in the BRUKINSA combination arm and 42% (95% CI: 23, 60) in the obinutuzumab monotherapy arm.

16 HOW SUPPLIED/STORAGE AND HANDLING

How Supplied

Strength | Description | Package Size | NDC Number
80 mg | white to off-white opaque capsule, marked with "ZANU 80" in black ink | 120-count capsules in a bottle with a child-resistant cap | 72579-011-02
160 mg | blue, oval, film-coated tablets debossed with "zanu" on one side and functional scoring on the other side | 60-count tablets in a bottle with a child-resistant cap | 72579-122-01

Storage

Store at 20°C to 25°C (68°F to 77°F); excursions permitted between 15°C and 30°C (59°F and 86°F) [See USP Controlled Room Temperature].

17 PATIENT COUNSELING INFORMATION

Advise patients to read the FDA-approved patient labeling (Patient Information).

Hemorrhage

Inform patients to report signs or symptoms of severe bleeding. Inform patients that BRUKINSA may need to be interrupted for major surgeries or procedures [see Warnings and Precautions (5.1)].

Infections

Inform patients to report signs or symptoms suggestive of infection [see Warnings and Precautions (5.2)].

Cytopenias

Inform patients that they will need periodic blood tests to check blood counts during treatment with BRUKINSA [see Warnings and Precautions (5.3)].

Second Primary Malignancies

Inform patients that other malignancies have been reported in patients who have been treated with BRUKINSA, including skin cancer and other solid tumors. Advise patients to use sun protection and have monitoring for development of other cancers [see Warnings and Precautions (5.4)].

Cardiac Arrhythmias

Counsel patients to report any signs of palpitations, lightheadedness, dizziness, fainting, shortness of breath, and chest discomfort [see Warnings and Precautions (5.5)].

Hepatotoxicity, Including Drug-Induced Liver Injury

Inform patients that liver problems, including drug-induced liver injury and abnormalities in liver tests, may develop during BRUKINSA treatment. Advise patients to contact their healthcare provider immediately if they experience abdominal discomfort, dark urine, or jaundice [see Warnings and Precautions (5.6)].

Embryo-Fetal Toxicity

Advise pregnant women and females of reproductive potential of the potential hazard to a fetus and to use effective contraception during treatment and for 1 week after the last dose of BRUKINSA [see Warnings and Precautions (5.7)]. Advise males with female sexual partners of reproductive potential to use effective contraception during BRUKINSA treatment and for 1 week after the last dose of BRUKINSA [see Use in Specific Populations (8.3)].

Lactation

Advise females not to breastfeed during treatment with BRUKINSA and for 2 weeks after the last dose [see Use in Specific Populations (8.2)].

Administration Instructions

- BRUKINSA capsules may be taken with or without food. Advise patients that BRUKINSA capsules should be swallowed whole with a glass of water and not to open, break, or chew the capsules [see Dosage and Administration (2.1)].
- BRUKINSA tablets may be taken with or without food. Advise patients that BRUKINSA tablets should be swallowed whole with a glass of water and not to chew or crush the tablets. Tablets can be split in half as prescribed by the healthcare provider [see Dosage and Administration (2.1)].

Missed Dose

Advise patients that if they miss a dose of BRUKINSA, they may still take it as soon as possible on the same day with a return to the normal schedule the following day [see Dosage and Administration (2.1)].

Drug Interactions

Advise patients to inform their healthcare providers of all concomitant medications, including over-the-counter medications, vitamins, and herbal products [see Drug Interactions (7.1)].

BRUKINSA Capsules:
Manufactured for:
BeOne Medicines USA, Inc.
Pennington, NJ 08534

BRUKINSA Tablets:
Manufactured for:
BeOne Medicines USA, Inc.
Pennington, NJ 08534
Manufactured by:
Catalent Pharma Solutions, LLC
Winchester, KY 40391

BRUKINSA® is a registered trademark owned by BeOne Medicines I GmbH or its affiliates.
© BeOne Medicines I GmbH, 2025. All Rights Reserved.

PATIENT INFORMATION

BRUKINSA® (BROO-kin-sah)
(zanubrutinib)
capsules

BRUKINSA® (BROO-kin-sah)
(zanubrutinib)
tablets

What is BRUKINSA?
BRUKINSA is a prescription medicine used to treat adults with:

- Mantle cell lymphoma (MCL) who have received at least one prior treatment for their cancer.
- Waldenström's macroglobulinemia (WM).
- Marginal zone lymphoma (MZL) when the disease has come back or did not respond to treatment and who have received at least one certain type of treatment.
- Chronic lymphocytic leukemia (CLL) or small lymphocytic lymphoma (SLL).
- Follicular lymphoma (FL), in combination with the medicine obinutuzumab, when the disease has come back or did not respond to treatment and who have received at least two prior treatments.

It is not known if BRUKINSA is safe and effective in children.

Before taking BRUKINSA, tell your healthcare provider about all of your medical conditions, including if you:

- have bleeding problems.
- have had recent surgery or plan to have surgery. Your healthcare provider may stop BRUKINSA for any planned medical, surgical, or dental procedure.
- have an infection or have been advised that you are at increased risk of infection.
- have or had heart rhythm problems.
- have high blood pressure.
- have liver problems, including a history of hepatitis B virus (HBV) infection.
- are pregnant or plan to become pregnant. BRUKINSA can harm your unborn baby.
  Females who are able to become pregnant:
  - You should avoid getting pregnant during treatment and for 1 week after the last dose of BRUKINSA.
  - Your healthcare provider may do a pregnancy test before starting treatment with BRUKINSA.
  - You should use effective birth control (contraception) during treatment and for 1 week after the last dose of BRUKINSA.
  - Tell your healthcare provider right away if you become pregnant or think you are pregnant during treatment with BRUKINSA.
  Males with female partners who are able to become pregnant:
  - You should avoid getting female partners pregnant during treatment and for 1 week after the last dose of BRUKINSA.
  - You should use effective birth control (contraception) during treatment and for 1 week after the last dose of BRUKINSA.
- are breastfeeding or plan to breastfeed. It is not known if BRUKINSA passes into your breast milk. Do not breastfeed during treatment with BRUKINSA and for 2 weeks after the last dose of BRUKINSA.

Tell your healthcare provider about all the medicines you take, including prescription and over-the-counter medicines, vitamins, and herbal supplements. Especially tell your healthcare provider if you take a blood thinner medicine. Taking BRUKINSA with certain other medications may affect how BRUKINSA works and can cause side effects.

How should I take BRUKINSA?

- Take BRUKINSA exactly as your healthcare provider tells you to take it.
- Do not change your dose or stop taking BRUKINSA unless your healthcare provider tells you to.
- Your healthcare provider may tell you to decrease your dose, temporarily stop, or completely stop taking BRUKINSA if you develop certain side effects.
- Take BRUKINSA with or without food.
- Swallow BRUKINSA capsules whole with a glass of water. Do not open, break, or chew the capsules.
- Swallow BRUKINSA tablets whole with a glass of water. Do not chew or crush the tablets.
  - BRUKINSA tablets can be split in half as prescribed by your healthcare provider.
- If you miss a dose of BRUKINSA, take it as soon as you remember on the same day. Return to your normal schedule the next day.

What are the possible side effects of BRUKINSA?
BRUKINSA may cause serious side effects, including:

- Bleeding problems (hemorrhage). Bleeding problems are common with BRUKINSA, and can be serious and may lead to death. Your risk of bleeding may increase if you are also taking a blood thinner medicine. Tell your healthcare provider if you develop any signs or symptoms of bleeding, including:

- blood in your stools or black stools (looks like tar)
- pink or brown urine
- unexpected bleeding, or bleeding that is severe or you cannot control
- vomit blood or vomit that looks like coffee grounds
- cough up blood or blood clots

- increased bruising
- dizziness
- weakness
- confusion
- change in speech
- headache that lasts a long time

- Infections that can be serious and may lead to death. Tell your healthcare provider right away if you develop fever, chills, or flu-like symptoms during your treatment with BRUKINSA.
- Decrease in blood cell counts (white blood cells, platelets, and red blood cells). Your healthcare provider should do blood tests during treatment with BRUKINSA to check your blood counts.
- Second primary cancers. New cancers have happened in people during treatment with BRUKINSA, including cancers of the skin or other organs. Your healthcare provider will check you for other cancers during treatment with BRUKINSA. Use sun protection when you are outside in sunlight.
- Heart rhythm problems. Serious heart problems, including atrial fibrillation, atrial flutter, and ventricular arrhythmias, have happened in people treated with BRUKINSA and may lead to death. Your risk for heart rhythm problems may be increased if you have high blood pressure or have had heart rhythm problems in the past or have a short-term (acute) infection. Tell your healthcare provider if you develop any of the following signs or symptoms:

- your heartbeat is fast or irregular
- feel lightheaded or dizzy
- pass out (faint)

- shortness of breath
- chest discomfort

- Liver problems. Liver problems, which may be severe or life-threatening, or lead to death, can happen in people treated with BRUKINSA. Your healthcare provider will do blood tests to check your liver before and during treatment with BRUKINSA. Tell your healthcare provider or get medical help right away if you develop any signs of liver problems, including stomach pain or discomfort, dark-colored urine, or yellow skin and eyes.

The most common side effects of BRUKINSA include:

- decreased white blood cell count
- decreased platelet count
- cold-like symptoms (upper respiratory tract infection)

- muscle, bone, or joint pain

These are not all the possible side effects of BRUKINSA.
Call your doctor for medical advice about side effects. You may report side effects to FDA at 1-800-FDA-1088.

How should I store BRUKINSA?

- Store BRUKINSA at room temperature between 68°F and 77°F (20°C and 25°C).
- BRUKINSA comes in a bottle with a child-resistant cap.

Keep BRUKINSA and all medicines out of the reach of children.

General information about the safe and effective use of BRUKINSA.
Medicines are sometimes prescribed for purposes other than those listed in a Patient Information leaflet. Do not use BRUKINSA for a condition for which it was not prescribed. Do not give BRUKINSA to other people, even if they have the same symptoms that you have. It may harm them. You can ask your healthcare provider or pharmacist for more information about BRUKINSA that is written for healthcare professionals.

What are the ingredients in BRUKINSA?
Active ingredient: zanubrutinib
Capsule inactive ingredients: colloidal silicon dioxide, croscarmellose sodium, magnesium stearate, microcrystalline cellulose, and sodium lauryl sulfate. The capsule shell contains edible black ink, gelatin, and titanium dioxide.
Tablet inactive ingredients: colloidal silicon dioxide, croscarmellose sodium, lactose monohydrate, magnesium stearate, microcrystalline cellulose, povidone, and sodium lauryl sulfate. The film-coating contains FD&C Blue No. 1, FD&C Blue No. 2, hypromellose, titanium dioxide, and triacetin.
BRUKINSA Capsules:
Manufactured for: BeOne Medicines USA, Inc., Pennington, NJ 08534
BRUKINSA Tablets:
Manufactured for: BeOne Medicines USA, Inc., Pennington, NJ 08534
Manufactured by: Catalent Pharma Solutions, LLC, Winchester, KY 40391
BRUKINSA® is a registered trademark owned by BeOne Medicines I GmbH or its affiliates.
© BeOne Medicines I GmbH, 2025. All Rights Reserved.
For more information, go to www.BRUKINSA.com or call 1-833-969-2463.

This Patient Information has been approved by the U.S. Food and Drug Administration.

Issued: 6/2025

PRINCIPAL DISPLAY PANEL - 80 mg Capsule Carton

NDC 72579-011-02
Rx only

Brukinsa®
zanubrutinib
capsules

80 mg

Swallow capsules whole.
Do not open, break or
chew the capsules.

120 capsules

PRINCIPAL DISPLAY PANEL - 160 mg Tablet Carton

Rx only

Brukinsa®
zanubrutinib
tablets

160 mg

Swallow tablets whole.
Do not crush or chew the tablets.

60 tablets